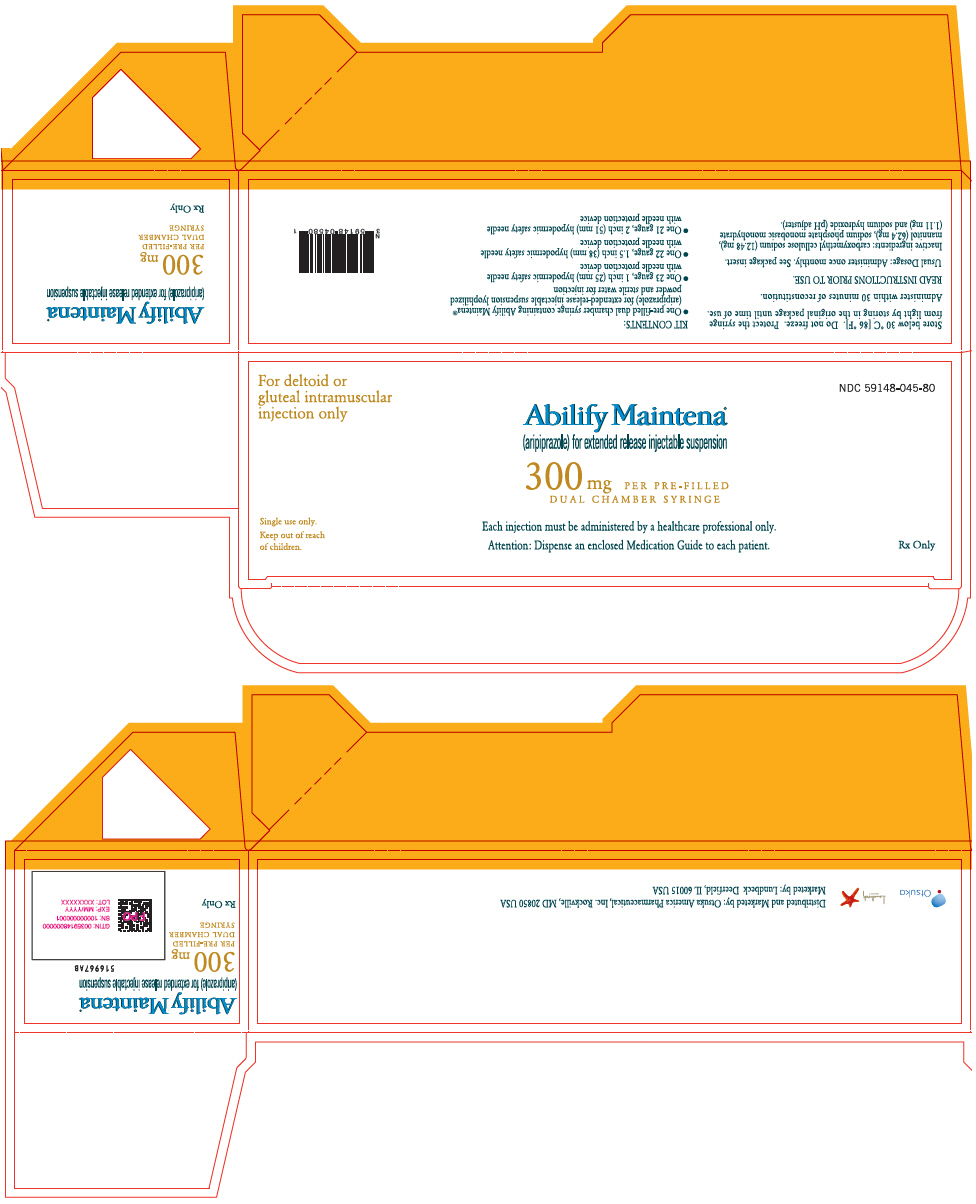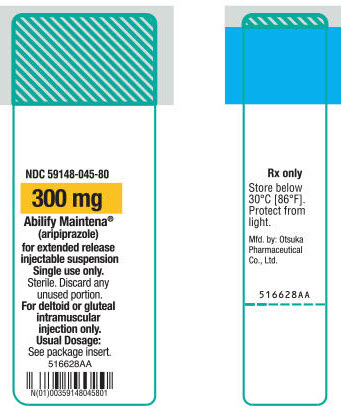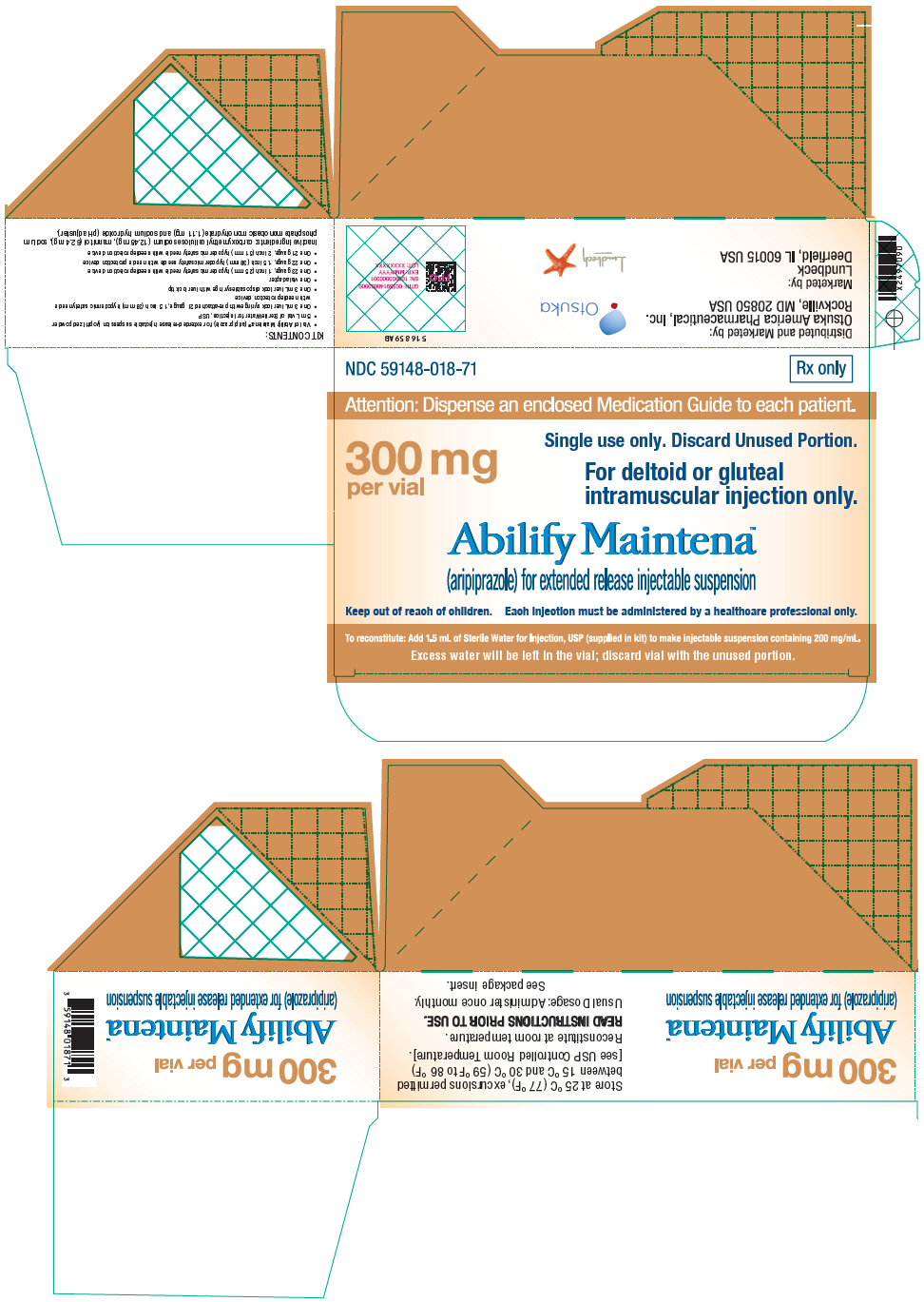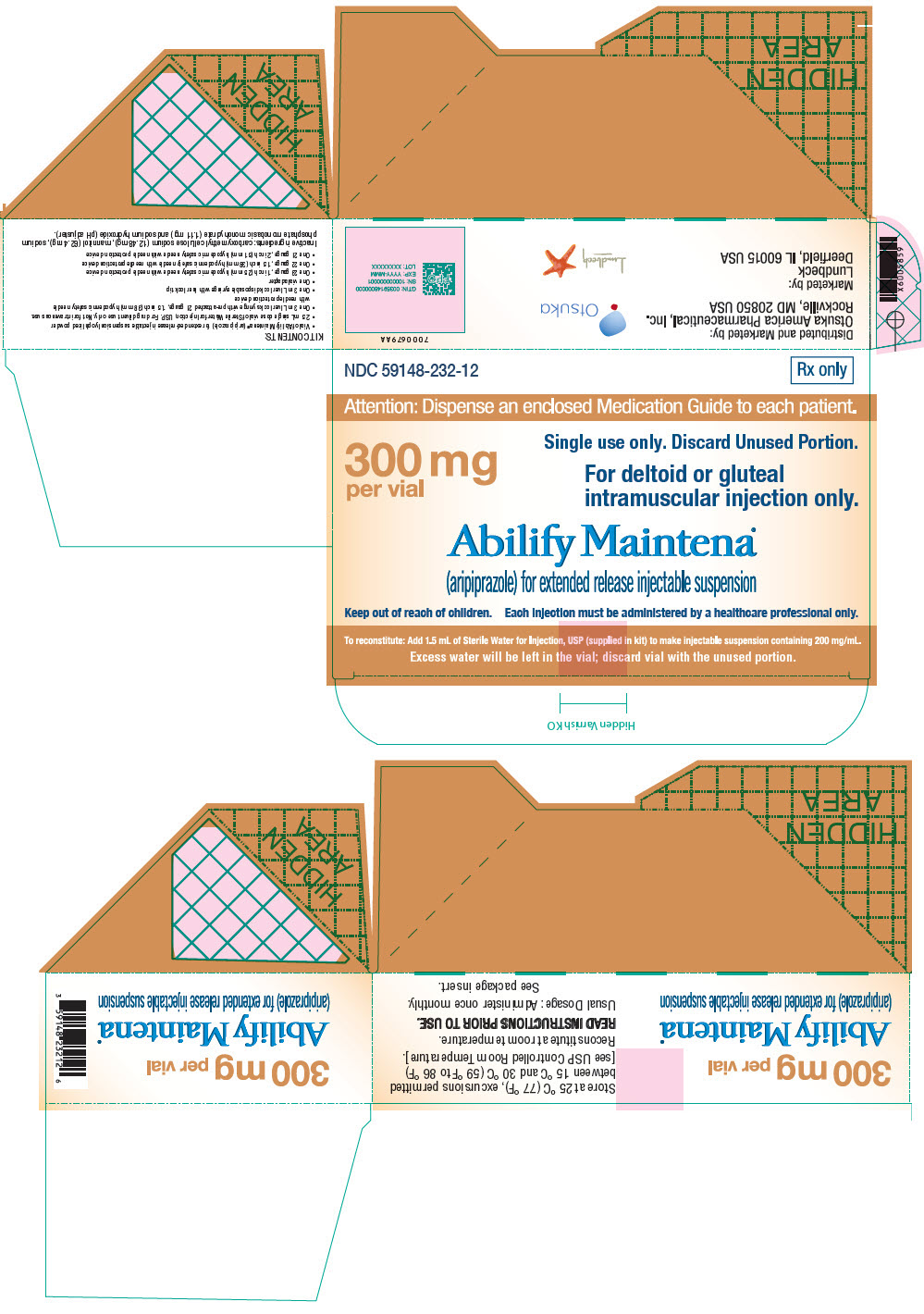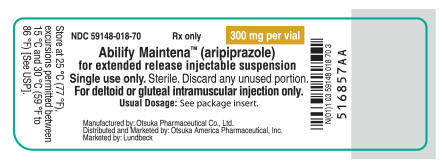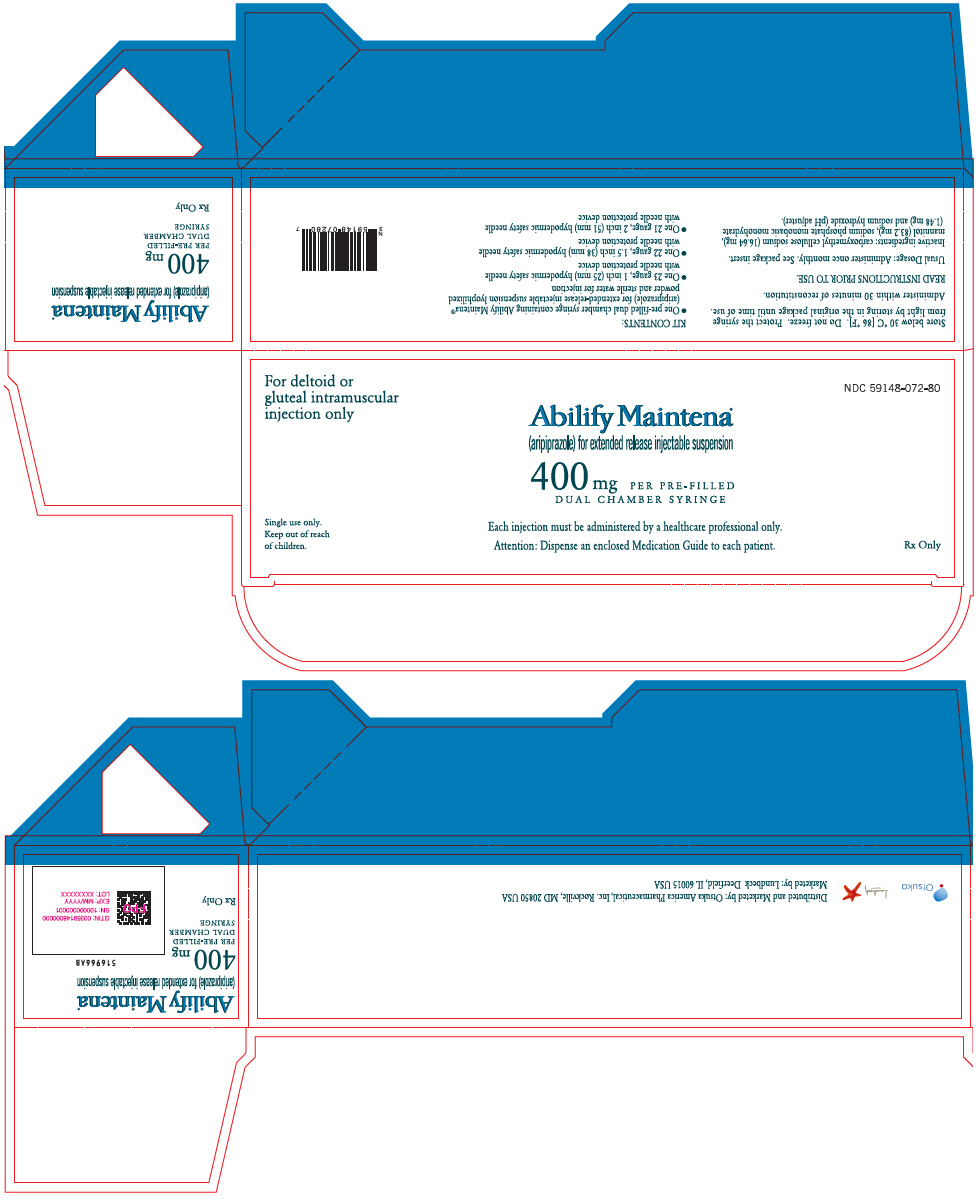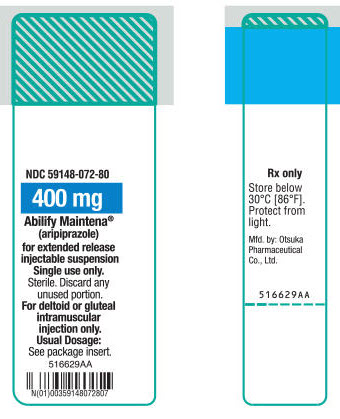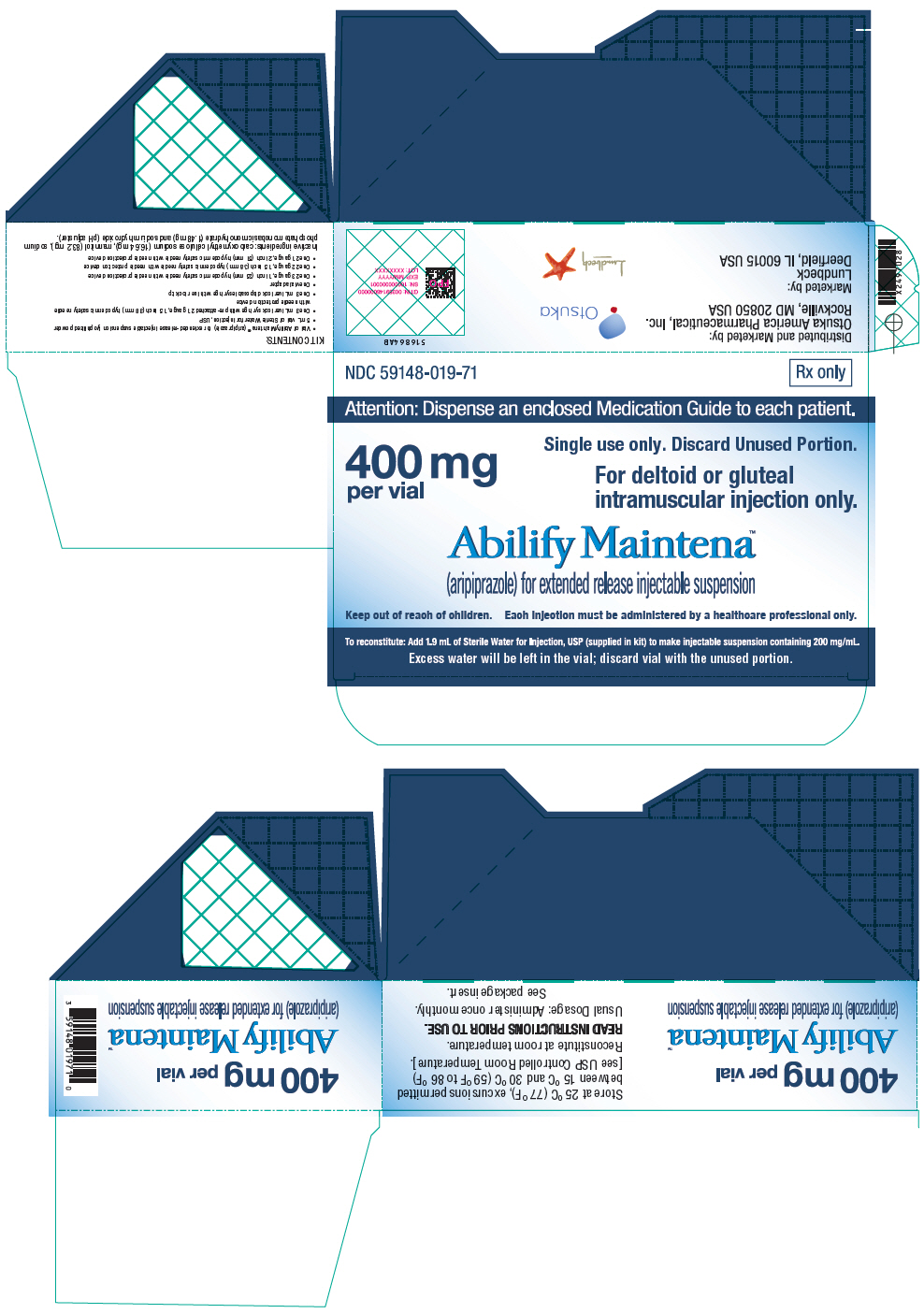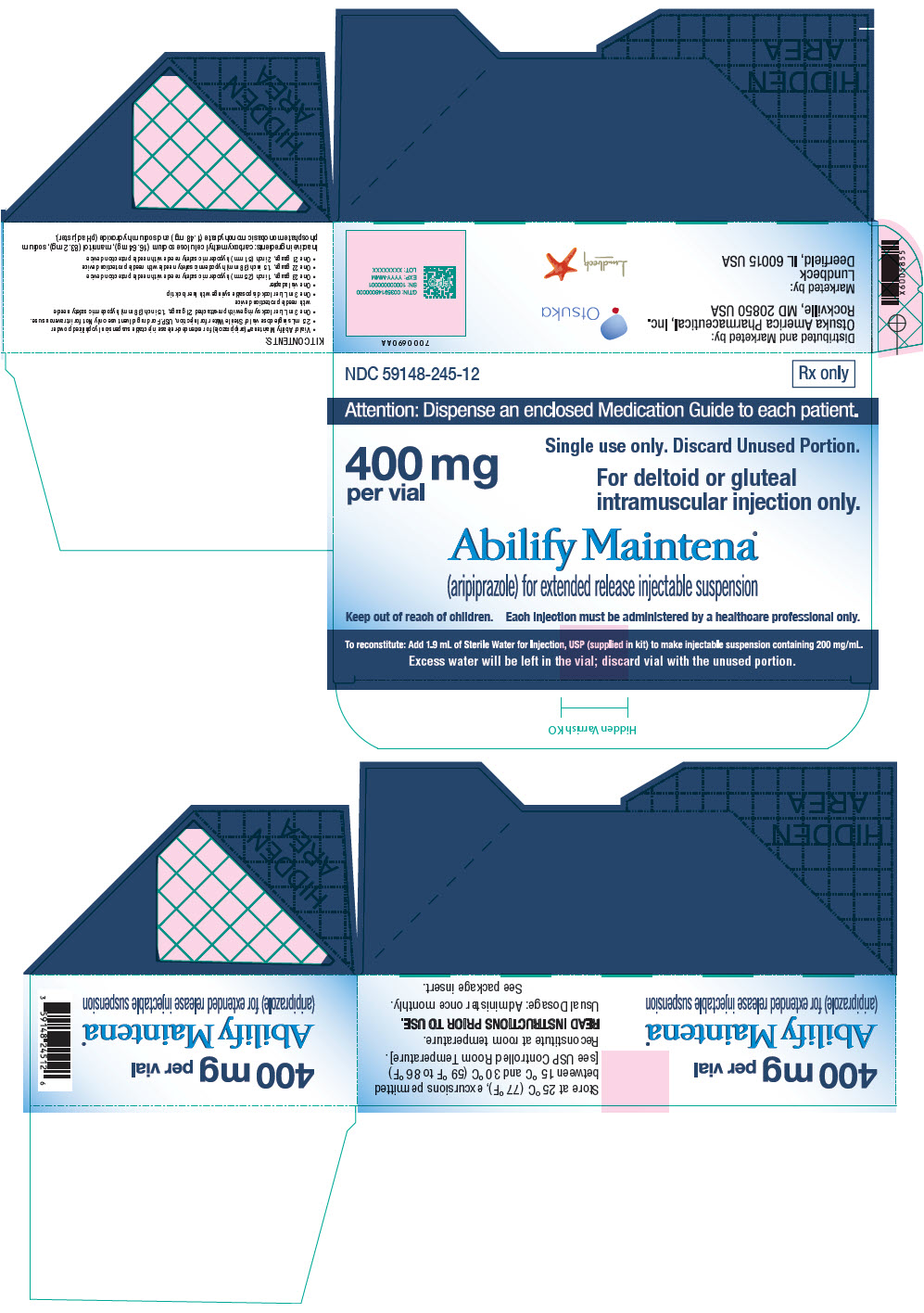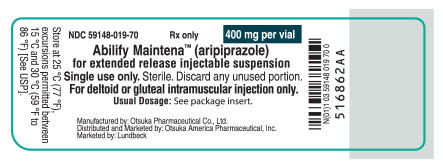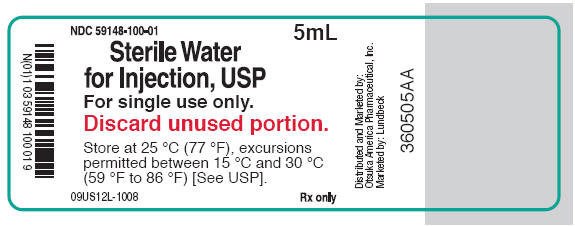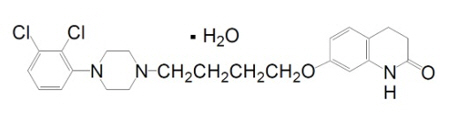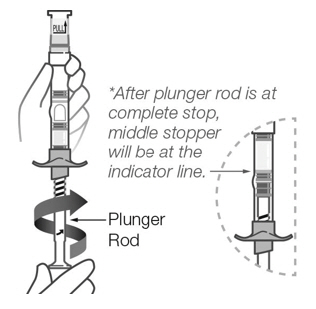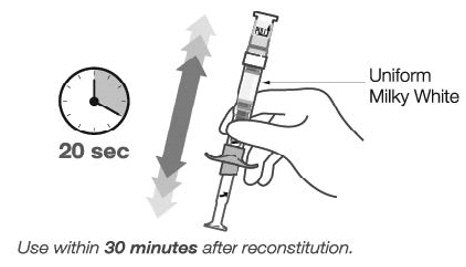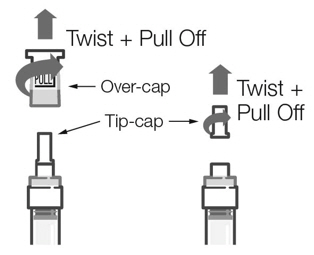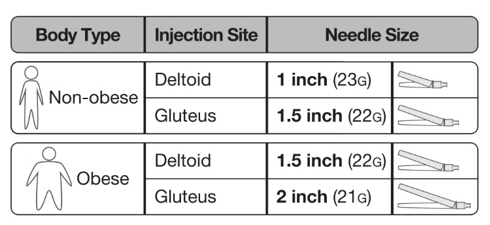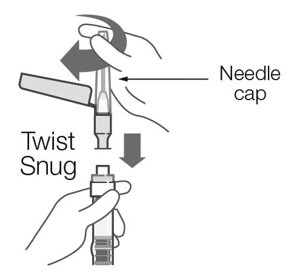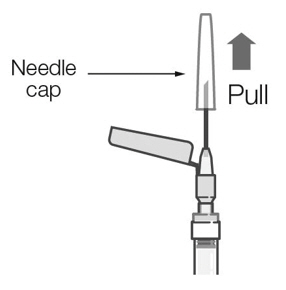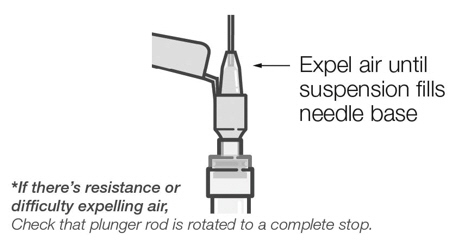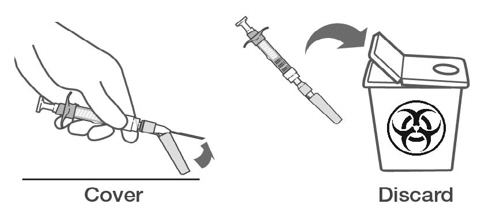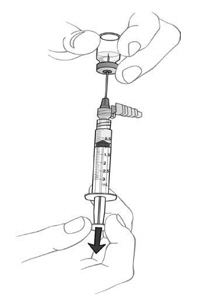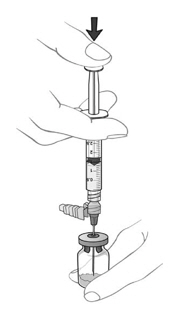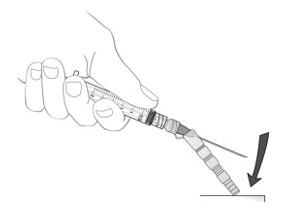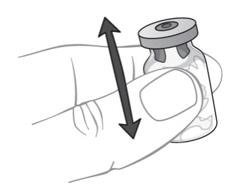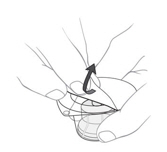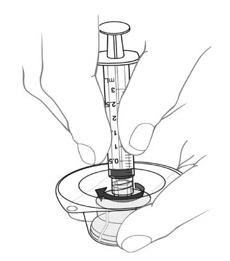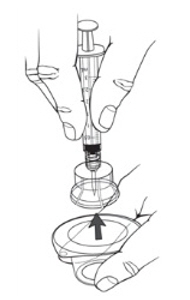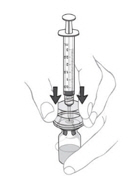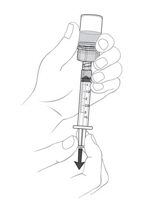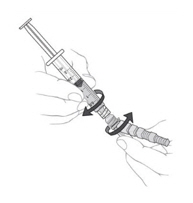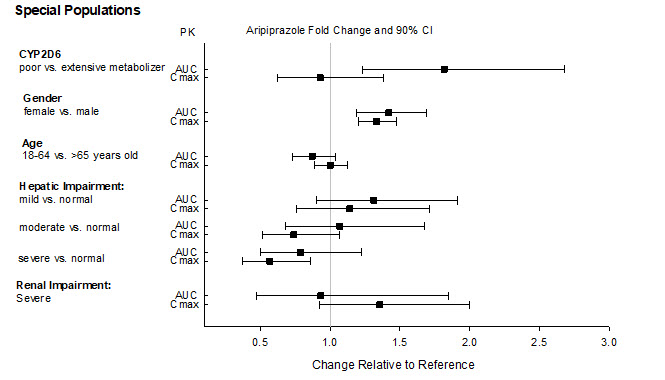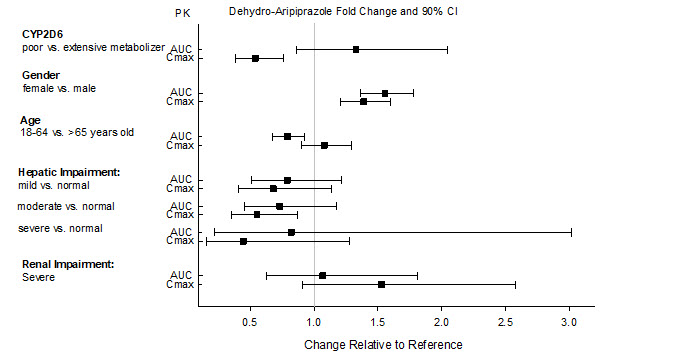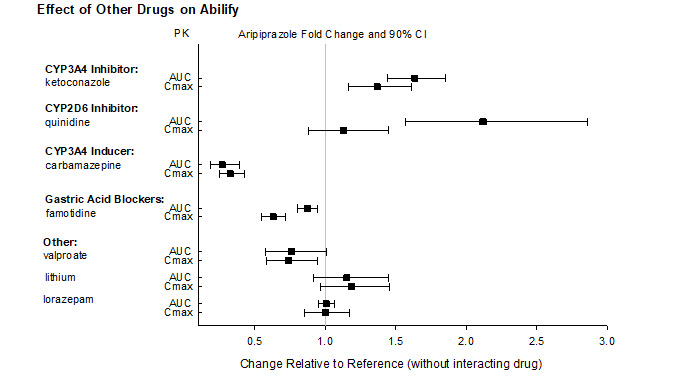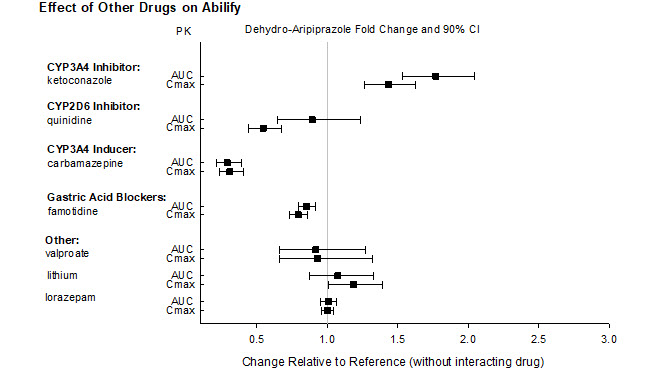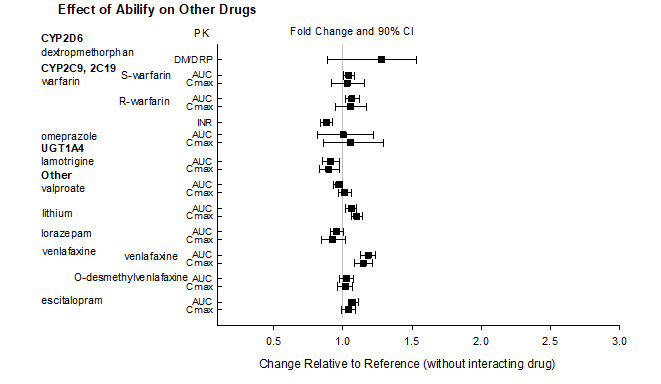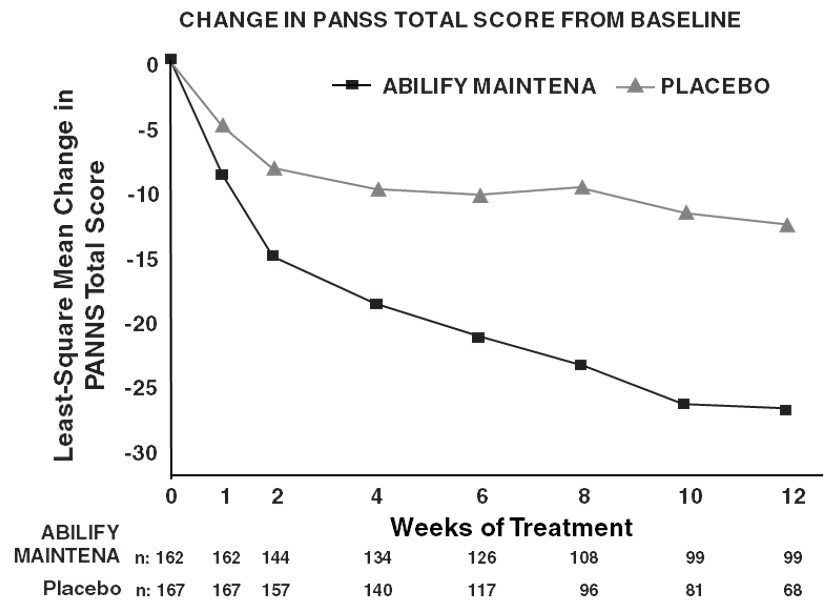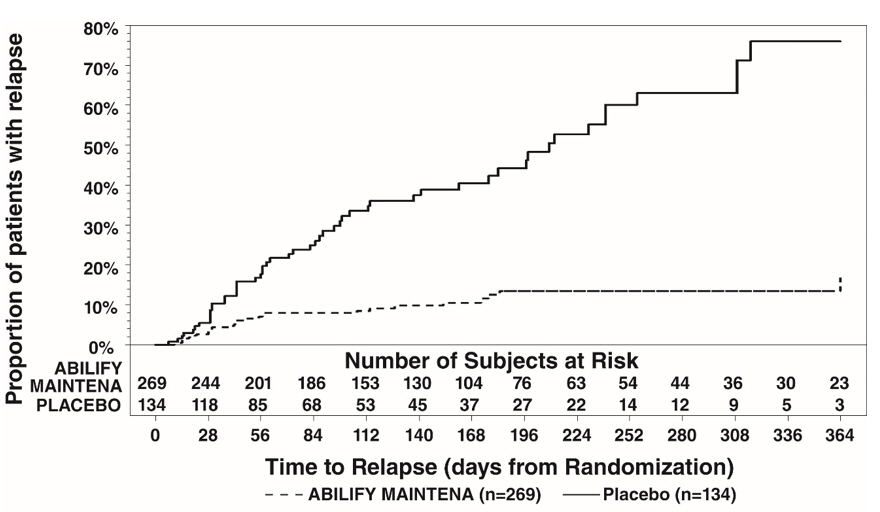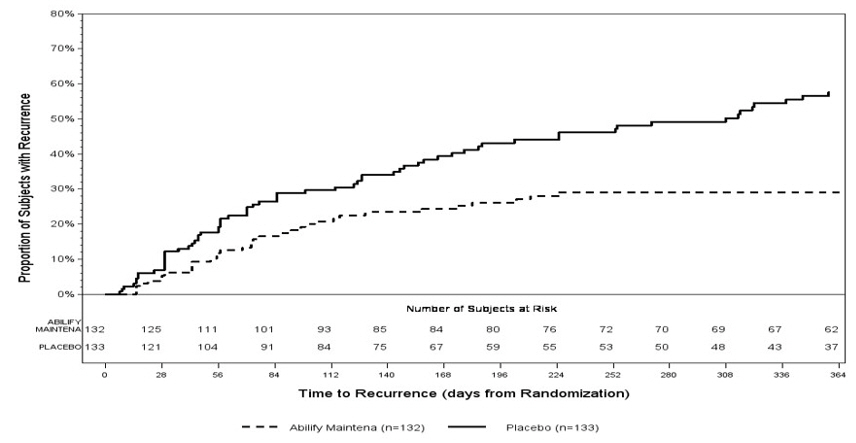 DRUG LABEL: ABILIFY MAINTENA
NDC: 59148-018 | Form: KIT | Route: INTRAMUSCULAR
Manufacturer: Otsuka America Pharmaceutical, Inc.
Category: prescription | Type: HUMAN PRESCRIPTION DRUG LABEL
Date: 20250415

ACTIVE INGREDIENTS: ARIPIPRAZOLE 300 mg/1.5 mL
INACTIVE INGREDIENTS: CARBOXYMETHYLCELLULOSE SODIUM, UNSPECIFIED; MANNITOL; SODIUM PHOSPHATE, MONOBASIC, MONOHYDRATE; SODIUM HYDROXIDE; WATER

HIGHLIGHTS OF PRESCRIBING INFORMATION

These highlights do not include all the information needed to use ABILIFY MAINTENA safely and effectively. See full prescribing information for ABILIFY MAINTENA.
ABILIFY MAINTENA® (aripiprazole) for extended-release injectable suspension, for intramuscular use
Initial U.S. Approval: 2002

WARNING: INCREASED MORTALITY IN ELDERLY PATIENTS WITH DEMENTIA-RELATED PSYCHOSIS

See full prescribing information for complete boxed warning.

- Elderly patients with dementia-related psychosis treated with antipsychotic drugs are at an increased risk of death (5.1)
- ABILIFY MAINTENA is not approved for the treatment of patients with dementia-related psychosis (5.1)

RECENT MAJOR CHANGES

Dosage and Administration (2.7) | 1/2025
Dosage and Administration (2.1, 2.2, 2.3, 2.4, 2.5) | 3/2025
Warning and Precautions (5.11) | 3/2025

1 INDICATIONS AND USAGE

ABILIFY MAINTENA is an atypical antipsychotic indicated:

- for treatment of schizophrenia in adults (1)
- for maintenance monotherapy treatment of bipolar I disorder in adults (1)

2 DOSAGE AND ADMINISTRATION

- Only to be administered by intramuscular injection in the deltoid or gluteal muscle by a healthcare professional (2.1)
- For patients naïve to aripiprazole, establish tolerability with oral aripiprazole prior to initiating ABILIFY MAINTENA (2.1)
- Recommended dosage is 400 mg administered monthly as a single injection. Dose can be reduced to 300 mg in patients with adverse reactions (2.2)
- There are two ways to initiate treatment with ABILIFY MAINTENA
  - 1-day initiation: Administer two separate intramuscular injections of ABILIFY MAINTENA 400 mg and a single oral dose of aripiprazole 20 mg (2.2)
  - 14-day initiation: In conjunction with first ABILIFY MAINTENA 400 mg dose, take 14 consecutive days of concurrent oral aripiprazole (10 mg to 20 mg) or current oral antipsychotic (2.2)
- Dosage adjustments are required for missed doses (2.3)
- Known CYP2D6 poor metabolizers: Recommended starting and maintenance dose is 300 mg administered monthly as a single injection (2.4)
- See full prescribing information for ABILIFY MAINTENA dosage modifications due to drug interactions (2.4).
- ABILIFY MAINTENA comes in two types of kits. See instructions for reconstitution/injection/disposal procedures for 1) Pre-filled Dual Chamber Syringe (2.6), and 2) Vials (2.7).

3 DOSAGE FORMS AND STRENGTHS

For extended-release injectable suspension: 300 mg and 400 mg strength lyophilized powder for reconstitution in (3):

- single-dose, pre-filled, dual chamber syringe
- single-dose vial

4 CONTRAINDICATIONS

Known hypersensitivity to aripiprazole (4)

5 WARNINGS AND PRECAUTIONS

- Cerebrovascular Adverse Reactions in Elderly Patients with Dementia-Related Psychosis: Increased incidence of cerebrovascular adverse reactions (e.g., stroke, transient ischemic attack, including fatalities) (5.2)
- Neuroleptic Malignant Syndrome: Manage with immediate discontinuation and close monitoring (5.3)
- Tardive Dyskinesia: Discontinue if clinically appropriate (5.4)
- Metabolic Changes: Atypical antipsychotic drugs have been associated with metabolic changes that may increase cardiovascular/cerebrovascular risk. These metabolic changes include hyperglycemia, dyslipidemia, and weight gain (5.5)
  - Hyperglycemia and Diabetes Mellitus: Monitor patients for symptoms of hyperglycemia including polydipsia, polyuria, polyphagia, and weakness. Monitor glucose regularly in patients with and at risk for diabetes (5.5)
  - Dyslipidemia: Undesirable alterations have been observed in patients treated with atypical antipsychotics (5.5)
  - Weight Gain: Gain in body weight has been observed; clinical monitoring of weight is recommended (5.5)
- Pathological Gambling and Other Compulsive Behaviors: Consider dose reduction or discontinuation (5.6)
- Orthostatic Hypotension: Use with caution in patients with known cardiovascular or cerebrovascular disease (5.7)
- Leukopenia, Neutropenia, and Agranulocytosis: Perform complete blood counts in patients with a history of a clinically significant low white blood cell count (WBC)/absolute neutrophil count (ANC). Consider discontinuation if clinically significant decline in WBC/ANC in the absence of other causative factors (5.9)
- Seizures: Use cautiously in patients with a history of seizures or with conditions that lower the seizure threshold (5.10)
- Potential for Cognitive and Motor Impairment: Use caution when operating machinery (5.11)

6 ADVERSE REACTIONS

Most commonly observed adverse reactions with ABILIFY MAINTENA in patients with schizophrenia (incidence ≥5% and at least twice that for placebo) were increased weight, akathisia, injection site pain, and sedation (6.1).

To report SUSPECTED ADVERSE REACTIONS, contact Otsuka America Pharmaceutical, Inc. at 1-800-438-9927 or FDA at 1-800-FDA-1088 or www.fda.gov/medwatch.

7 DRUG INTERACTIONS

- CYP2D6 inhibitors and CYP3A4 Inhibitors: See full prescribing information for ABILIFY MAINTENA dosage modifications when used concomitantly with CYP2D6 inhibitors and/or CYP3A4 inhibitors for greater than 14 days (7.1)
- CYP3A4 Inducers: Avoid concomitant use for greater than 14 days (7.1)
- See full prescribing information for additional clinically significant drug interactions (7.1)

8 USE IN SPECIFIC POPULATIONS

- Pregnancy: May cause extrapyramidal and/or withdrawal symptoms in neonates with third trimester exposure (8.1)
- Lactation: Monitor the breastfed infant for dehydration and lack of appropriate weight gain (8.2)

FULL PRESCRIBING INFORMATION

WARNING: INCREASED MORTALITY IN ELDERLY PATIENTS WITH DEMENTIA-RELATED PSYCHOSIS

Elderly patients with dementia-related psychosis treated with antipsychotic drugs are at an increased risk of death. ABILIFY MAINTENA is not approved for the treatment of patients with dementia-related psychosis [see Warnings and Precautions (5.1)].

1 INDICATIONS AND USAGE

ABILIFY MAINTENA (aripiprazole) is indicated:

- for the treatment of schizophrenia in adults
- for maintenance monotherapy treatment of bipolar I disorder in adults

2 DOSAGE AND ADMINISTRATION

2.1 Important Administration Information

For patients who have never taken aripiprazole, establish tolerability with oral aripiprazole prior to initiating treatment with ABILIFY MAINTENA. Due to the half-life of oral aripiprazole (i.e., 75 hours and 94 hours for aripiprazole and dehydro-aripiprazole, respectively), it may take up to 2 weeks to fully assess tolerability.

ABILIFY MAINTENA must be administered by intramuscular injection by a healthcare professional. Do not administer by any other route.

For detailed preparation and administration instructions, [see Dosage and Administration (2.6, 2.7)].

2.2 Recommended Dosage for ABILIFY MAINTENA

The recommended dose of ABILIFY MAINTENA is 400 mg monthly (no sooner than 26 days after the previous injection).

There are two ways to initiate treatment with ABILIFY MAINTENA in patients receiving oral antipsychotics:

1-day initiation:

- Administer two intramuscular injections of ABILIFY MAINTENA 400 mg in two different injection sites (in either the deltoid or gluteal muscle), and one dose of oral aripiprazole 20 mg on the first day of treatment with ABILIFY MAINTENA.
- Do not administer both injections into the same muscle.

14-day initiation:

- When ABILIFY MAINTENA injection is initiated in patients receiving oral aripiprazole administer one intramuscular injection of ABILIFY MAINTENA 400 mg in either the deltoid or gluteal muscle and continue treatment with oral aripiprazole (10 mg to 20 mg) for 14 consecutive days to achieve therapeutic aripiprazole concentrations during initiation of therapy.
- For patients already stable on another oral antipsychotic (and known to tolerate aripiprazole), administer one intramuscular injection of ABILIFY MAINTENA 400 mg in either the deltoid or gluteal muscle and continue treatment with the oral antipsychotic for 14 consecutive days to maintain therapeutic antipsychotic concentrations during initiation of therapy.

If there are adverse reactions with the 400 mg dosage, the dosage may be reduced to 300 mg once monthly.

2.3 Missed Doses

If the second or third doses are missed:

- If more than 4 weeks and less than 5 weeks have elapsed since the last injection, administer the injection as soon as possible.
- If more than 5 weeks have elapsed since the last injection, restart treatment with either 1-day initiation or 14-day initiation with ABILIFY MAINTENA [see Dosage and Administration (2.2)].

If the fourth or subsequent doses are missed:

- If more than 4 weeks and less than 6 weeks have elapsed since the last injection, administer the injection as soon as possible.
- If more than 6 weeks have elapsed since the last injection, restart treatment with either 1-day initiation or 14-day initiation with ABILIFY MAINTENA [see Dosage and Administration (2.2)].

2.4 Dosage Modifications for Cytochrome P450 Considerations

Refer to Table 1 and Table 2 for dosage modifications for patients who are CYP2D6 poor metabolizers and/or in patients taking concomitant CYP3A4 inhibitors or CYP2D6 inhibitors for greater than 14 days.

If the CYP3A4 inhibitor or CYP2D6 inhibitor is withdrawn, the ABILIFY MAINTENA dosage may need to be increased to the previous dose [see Dosage and Administration (2.2)].

Avoid the concomitant use of CYP3A4 inducers with ABILIFY MAINTENA for greater than 14 days because the blood levels of aripiprazole are decreased and may be below the effective levels.

Dosage modifications are not recommended for patients with concomitant use of CYP3A4 inhibitors, CYP2D6 inhibitors or CYP3A4 inducers for less than 14 days.

Table 1: Dosage Modifications for ABILIFY MAINTENA (1-Day Initiation) in Patients who are known CYP2D6 Poor Metabolizers and Patients Taking Concomitant CYP2D6 Inhibitors, 3A4 Inhibitors, and/or CYP3A4 Inducers for Greater than 14 days
Factors | Adjusted Dose [No change for oral dosage required during initiation.]
CYP2D6 Poor Metabolizers
Known CYP2D6 Poor Metabolizers | 300 mg
Known CYP2D6 Poor Metabolizers taking concomitant CYP3A4 inhibitors | Avoid use
Concomitant use with CYP Inhibitors and/or Inducers
Strong CYP2D6 or CYP3A4 inhibitors | 300 mg
CYP2D6 and CYP3A4 inhibitors | Avoid use
CYP3A4 inducers | Avoid use

Table 2: Dosage Modifications for ABILIFY MAINTENA (14-Day Initiation) in Patients who are known CYP2D6 Poor Metabolizers and Patients Taking Concomitant CYP2D6 Inhibitors, 3A4 Inhibitors, and/or CYP3A4 Inducers for Greater than 14 days
Factors | Adjusted Dose [No change for oral dosage required during initiation.]
CYP2D6 Poor Metabolizers
Known CYP2D6 Poor Metabolizers | 300 mg
Known CYP2D6 Poor Metabolizers taking concomitant CYP3A4 inhibitors | 200 mg [200 mg and 160 mg dosage adjustment is obtained only by using the 300 mg or 400 mg strength vials.]
Patients Taking 400 mg of ABILIFY MAINTENA
Strong CYP2D6 or CYP3A4 inhibitors | 300 mg
CYP2D6 and CYP3A4 inhibitors | 200 mg
CYP3A4 inducers | Avoid use
Patients Taking 300 mg of ABILIFY MAINTENA
Strong CYP2D6 or CYP3A4 inhibitors | 200 mg
CYP2D6 and CYP3A4 inhibitors | 160 mg
CYP3A4 inducers | Avoid use

ABILIFY MAINTENA comes in two types of kits. See instructions for reconstitution/injection/disposal procedures for 1) Pre-filled Dual Chamber Syringe [see Dosage and Administration (2.6)], and 2) Vials [see Dosage and Administration (2.7)].

2.5 Aripiprazole Formulations and Kits

ABILIFY MAINTENA comes in two types of kits. See instructions for reconstitution/injection/disposal procedures for 1) Pre-filled Dual Chamber Syringe available in 300 mg or 400 mg strength syringes [see Dosage and Administration (2.6)], and 2) Single-dose vials available in 300 mg or 400 mg strength vials [see Dosage and Administration (2.7)].

The 200 mg and 160 mg dosage adjustments are obtained only by using the 300 mg or 400 mg strength vials.

2.6 Pre-filled Dual Chamber Syringe: Preparation and Administration Instructions

Preparation Prior to Reconstitution

For deep intramuscular deltoid or gluteal injection by healthcare professionals only. Do not administer by any other route. Inject full syringe contents immediately following reconstitution. Administer once monthly.

Lay out and confirm that components listed below are provided in the kit:

- One ABILIFY MAINTENA (aripiprazole) pre-filled dual chamber syringe (400 mg or 300 mg as appropriate) for extended-release injectable suspension containing lyophilized powder and Sterile Water for Injection
- One 23-gauge, 1-inch (25 mm) hypodermic safety needle with needle protection device for deltoid administration in non-obese patients
- One 22-gauge, 1.5-inch (38 mm) hypodermic safety needle with needle protection device for gluteal administration in non-obese patients or deltoid administration in obese patients
- One 21-gauge, 2-inch (51 mm) hypodermic safety needle with needle protection device for gluteal administration in obese patients

Reconstitution of Lyophilized Powder in Pre-filled Dual Chamber Syringe

Reconstitute at room temperature.

a) Push plunger rod slightly to engage threads. And then, rotate plunger rod until the rod stops rotating to release diluent. After plunger rod is at complete stop, middle stopper will be at the indicator line (see Figure 1).
  Figure 1
b) Vertically shake the syringe vigorously for 20 seconds until drug is uniformly milky-white (see Figure 2).
  Figure 2
c) Visually inspect the syringe for particulate matter and discoloration prior to administration. The reconstituted ABILIFY MAINTENA suspension should appear to be a uniform, homogeneous suspension that is opaque and milky-white in color.

Injection Procedure

Use appropriate aseptic techniques throughout injection procedure. For deep intramuscular injection only.

a) Twist and pull off Over-cap and Tip-cap (see Figure 3).
  Figure 3
b) Select appropriate needle (see Figure 4).
  Figure 4
  For deltoid administration:
  - 23-gauge, 1-inch (25 mm) hypodermic safety needle with needle protection device for non-obese patients
  - 22-gauge, 1.5-inch (38 mm) hypodermic safety needle with needle protection device for obese patients
  For gluteal administration:
  - 22-gauge, 1.5-inch (38 mm) hypodermic safety needle with needle protection device for non-obese patients
  - 21-gauge, 2-inch (51 mm) hypodermic safety needle with needle protection device for obese patients

c) While holding the needle cap, ensure the needle is firmly seated on the safety device with a push. Twist clockwise until SNUGLY fitted (see Figure 5).
  Figure 5
d) Then PULL needle-cap straight up (see Figure 6).
  Figure 6
e) Hold syringe UPRIGHT and ADVANCE PLUNGER ROD SLOWLY TO EXPEL THE AIR. Expel air until suspension fills needle base. If it's not possible to advance plunger rod to expel the air, check that plunger rod is rotated to a complete stop (see Figure 7).
  Figure 7
f) Inject slowly into the deltoid or gluteal muscle. Do not massage the injection site.

Disposal Procedure

a) Engage the needle safety device and safely discard all kit components (see Figure 8). ABILIFY MAINTENA pre-filled dual chamber syringe is for single-use only.
  Figure 8
b) Rotate sites of injections between the two deltoid or gluteal muscles.

2.7 Vial: Preparation and Administration Instructions

Preparation Prior to Reconstitution

For deep intramuscular injection by healthcare professionals only. Do not administer by any other route. Inject immediately after reconstitution. Administer once monthly.

a) Lay out and confirm that components listed below are provided in the kit:
  - Vial of ABILIFY MAINTENA (aripiprazole) for extended-release injectable suspension lyophilized powder
  - 2.5 mL or 5 mL single-dose vial of Sterile Water for Injection, USP. For drug diluent use only. Not for intravenous use.
  - One 3 mL, luer lock syringe with pre-attached 21-gauge, 1.5-inch (38 mm) hypodermic safety needle with needle protection device
  - One 3 mL, luer lock disposable syringe with luer lock tip
  - One vial adapter
  - One 23-gauge, 1-inch (25 mm) hypodermic safety needle with needle protection device for deltoid administration in non-obese patients
  - One 22-gauge, 1.5-inch (38 mm) hypodermic safety needle with needle protection device for gluteal administration in non-obese patients or deltoid administration in obese patients
  - One 21-gauge, 2-inch (51 mm) hypodermic safety needle with needle protection device for gluteal administration in obese patients
b) ABILIFY MAINTENA should be suspended using the Sterile Water for Injection as supplied in the kit.
c) The Sterile Water for Injection and ABILIFY MAINTENA vials are for single-dose only.
d) Use appropriate aseptic techniques throughout reconstitution and reconstitute at room temperature.
e) Select the amount of Sterile Water for Injection needed for reconstitution (see Table 3).

Table 3: Amount of Sterile Water for Injection Needed for Reconstitution
400 mg Vial |  | 300 mg Vial
Dose | Sterile Water for Injection | Dose | Sterile Water for Injection
400 mg | 1.9 mL | 300 mg | 1.5 mL

Important: There is more Sterile Water for Injection in the vial than is needed to reconstitute ABILIFY MAINTENA (aripiprazole) for extended-release injectable suspension. The vial will have excess Sterile Water for Injection; discard any unused portion.

Reconstitution of Lyophilized Powder in Vial

a) Remove the cap of the vial of Sterile Water for Injection and remove the cap of the vial containing ABILIFY MAINTENA lyophilized powder and wipe the tops with a sterile alcohol swab.
b) Using the syringe with pre-attached hypodermic safety needle, withdraw the pre-determined Sterile Water for Injection volume from the vial of Sterile Water for Injection into the syringe (see Figure 9). Residual Sterile Water for Injection will remain in the vial following withdrawal; discard any unused portion.
  Figure 9
c) Slowly inject the Sterile Water for Injection into the vial containing the ABILIFY MAINTENA lyophilized powder (see Figure 10).
  Figure 10
d) Withdraw air to equalize the pressure in the vial by pulling back slightly on the plunger. Subsequently, remove the needle from the vial. Engage the needle safety device by using the one-handed technique (see Figure 11). Gently press the sheath against a flat surface until the needle is firmly engaged in the needle protection sheath. Visually confirm that the needle is fully engaged into the needle protection sheath, and discard.
  Figure 11
e) Shake the vial vigorously for 30 seconds until the reconstituted suspension appears uniform (see Figure 12).
  Figure 12
f) Visually inspect the reconstituted suspension for particulate matter and discoloration prior to administration. The reconstituted ABILIFY MAINTENA is a uniform, homogeneous suspension that is opaque and milky-white in color.
g) If the injection is not performed immediately after reconstitution keep the vial at room temperature and shake the vial vigorously for at least 60 seconds to re-suspend prior to injection.
h) Do not store the reconstituted suspension in a syringe.

Preparation Prior to Injection

a) Use appropriate aseptic techniques throughout injection of the reconstituted ABILIFY MAINTENA suspension.
b) Remove the cover from the vial adapter package (see Figure 13). Do not remove the vial adapter from the package.
  Figure 13
c) Using the vial adapter package to handle the vial adapter, attach the prepackaged luer lock syringe to the vial adapter (see Figure 14).
  Figure 14
d) Use the luer lock syringe to remove the vial adapter from the package and discard the vial adapter package (see Figure 15). Do not touch the spike tip of the adapter at any time.
  Figure 15
e) Determine the recommended volume for injection (Table 4).

Table 4: ABILIFY MAINTENA Reconstituted Suspension Volume to Inject
400 mg Vial |  | 300 mg Vial
Dose | Volume to Inject | Dose | Volume to Inject
400 mg | 2 mL | --- | ---
300 mg | 1.5 mL | 300 mg | 1.5 mL
200 mg | 1 mL | 200 mg | 1 mL
160 mg | 0.8 mL | 160 mg | 0.8 mL

f) Wipe the top of the vial of the reconstituted ABILIFY MAINTENA suspension with a sterile alcohol swab.
g) Place and hold the vial of the reconstituted ABILIFY MAINTENA suspension on a hard surface. Attach the adapter-syringe assembly to the vial by holding the outside of the adapter and pushing the adapter's spike firmly through the rubber stopper, until the adapter snaps in place (see Figure 16).
  Figure 16
h) Slowly withdraw the recommended volume from the vial into the luer lock syringe to allow for injection (see Figure 17). A small amount of excess product will remain in the vial.
  Figure 17

Injection Procedure

a) Detach the luer lock syringe containing the recommended volume of reconstituted ABILIFY MAINTENA suspension from the vial.
b) Select the appropriate hypodermic safety needle and attach the needle to the luer lock syringe containing the suspension for injection. While holding the needle cap, ensure the needle is firmly seated on the safety device with a push. Twist clockwise until snugly fitted and then pull the needle cap straight away from the needle (see Figure 18).

For deltoid administration:

- 23-gauge, 1-inch (25 mm) hypodermic safety needle with needle protection device for non-obese patients
- 22-gauge, 1.5-inch (38 mm) hypodermic safety needle with needle protection device for obese patients

For gluteal administration:

- 22-gauge, 1.5-inch (38 mm) hypodermic safety needle with needle protection device for non-obese patients
- 21-gauge, 2-inch (51 mm) hypodermic safety needle with needle protection device for obese patients
  Figure 18

(c) Slowly inject the recommended volume as a single intramuscular injection into the deltoid or gluteal muscle. Do not massage the injection site.

Disposal Procedure

a) Engage the needle safety device as described in Section 2.6, Step (d) of Reconstitution of Lyophilized Powder in Vial and safely discard all kit components (see Figure 8). Dispose of the vials, adapter, needles, and syringe appropriately after injection. The Sterile Water for Injection and ABILIFY MAINTENA vials are for single-dose only.
b) Rotate sites of injections between the two deltoid or gluteal muscles.

3 DOSAGE FORMS AND STRENGTHS

For extended-release injectable suspension: 300 mg and 400 mg of lyophilized powder for reconstitution in:

- single-dose, pre-filled, dual chamber syringe
- single-dose vial

The reconstituted extended-release injectable suspension is a uniform, homogeneous suspension that is opaque and milky-white in color.

4 CONTRAINDICATIONS

ABILIFY MAINTENA is contraindicated in patients with a known hypersensitivity to aripiprazole. Hypersensitivity reactions ranging from pruritus/urticaria to anaphylaxis have been reported in patients receiving aripiprazole [see Adverse Reactions (6.1 and 6.2)].

5 WARNINGS AND PRECAUTIONS

5.1 Increased Mortality in Elderly Patients with Dementia- Related Psychosis

Elderly patients with dementia-related psychosis treated with antipsychotic drugs are at an increased risk of death. Analyses of 17 placebo-controlled trials (modal duration of 10 weeks), largely in patients taking atypical antipsychotic drugs, revealed a risk of death in drug-treated patients of between 1.6 to 1.7 times the risk of death in placebo-treated patients. Over the course of a typical 10-week controlled trial, the rate of death in drug-treated patients was about 4.5%, compared to a rate of about 2.6% in the placebo group.

Although the causes of death were varied, most of the deaths appeared to be either cardiovascular (e.g., heart failure, sudden death) or infectious (e.g., pneumonia) in nature. Observational studies suggest that, similar to atypical antipsychotic drugs, treatment with conventional antipsychotic drugs may increase mortality. The extent to which the findings of increased mortality in observational studies may be attributed to the antipsychotic drug as opposed to some characteristic(s) of the patients is not clear. ABILIFY MAINTENA is not approved for the treatment of patients with dementia-related psychosis.

5.2 Cerebrovascular Adverse Reactions, Including Stroke in Elderly Patients with Dementia-Related Psychosis

In placebo-controlled clinical studies (two flexible-dose and one fixed-dose study) of dementia-related psychosis, there was an increased incidence of cerebrovascular adverse reactions (e.g., stroke, transient ischemic attack), including fatalities, in oral aripiprazole-treated patients (mean age: 84 years; range: 78 to 88 years). In the fixed-dose study, there was a statistically significant dose response relationship for cerebrovascular adverse reactions in patients treated with oral aripiprazole. ABILIFY MAINTENA is not approved for the treatment of patients with dementia-related psychosis.

5.3 Neuroleptic Malignant Syndrome

A potentially fatal symptom complex sometimes referred to as Neuroleptic Malignant Syndrome (NMS) may occur with administration of antipsychotic drugs, including ABILIFY MAINTENA. Rare cases of NMS occurred during aripiprazole treatment in the worldwide clinical database.

Clinical manifestations of NMS are hyperpyrexia, muscle rigidity, altered mental status, and evidence of autonomic instability (irregular pulse or blood pressure, tachycardia, diaphoresis, and cardiac dysrhythmia). Additional signs may include elevated creatine phosphokinase, myoglobinuria (rhabdomyolysis), and acute renal failure.

The diagnostic evaluation of patients with this syndrome is complicated. In arriving at a diagnosis, it is important to exclude cases where the clinical presentation includes both serious medical illness (e.g., pneumonia, systemic infection) and untreated or inadequately treated extrapyramidal signs and symptoms (EPS). Other important considerations in the differential diagnosis include central anticholinergic toxicity, heat stroke, drug fever, and primary central nervous system pathology.

The management of NMS should include: 1) immediate discontinuation of antipsychotic drugs and other drugs not essential to concurrent therapy; 2) intensive symptomatic treatment and medical monitoring; and 3) treatment of any concomitant serious medical problems for which specific treatments are available. There is no general agreement about specific pharmacological treatment regimens for uncomplicated NMS.

If a patient requires antipsychotic drug treatment after recovery from NMS, the potential reintroduction of drug therapy should be carefully considered. The patient should be carefully monitored, since recurrences of NMS have been reported.

5.4 Tardive Dyskinesia

A syndrome of potentially irreversible, involuntary, dyskinetic movements may develop in patients treated with antipsychotic drugs. Although the prevalence of the syndrome appears to be highest among the elderly, especially elderly women, it is impossible to rely upon prevalence estimates to predict, at the inception of antipsychotic treatment, which patients are likely to develop the syndrome. Whether antipsychotic drug products differ in their potential to cause tardive dyskinesia is unknown.

The risk of developing tardive dyskinesia and the likelihood that it will become irreversible are believed to increase as the duration of treatment and the total cumulative dose of antipsychotic drugs administered to the patient increase. However, the syndrome can develop, although much less commonly, after relatively brief treatment periods at low doses.

Tardive dyskinesia may remit, partially or completely, if antipsychotic treatment is withdrawn. Antipsychotic treatment, itself, however, may suppress (or partially suppress) the signs and symptoms of the syndrome and, thereby, may possibly mask the underlying process. The effect of symptomatic suppression on the long-term course of the syndrome is unknown.

Given these considerations, ABILIFY MAINTENA should be prescribed in a manner that is most likely to minimize the occurrence of tardive dyskinesia. Chronic antipsychotic treatment should generally be reserved for patients who suffer from a chronic illness that 1) is known to respond to antipsychotic drugs and 2) for whom alternative, equally effective, but potentially less harmful treatments are not available or appropriate. In patients who do require chronic treatment, the smallest dose and the shortest duration of treatment producing a satisfactory clinical response should be sought. The need for continued treatment should be reassessed periodically.

If signs and symptoms of tardive dyskinesia appear in a patient treated with ABILIFY MAINTENA drug discontinuation should be considered. However, some patients may require treatment with ABILIFY MAINTENA despite the presence of the syndrome.

5.5 Metabolic Changes

Atypical antipsychotic drugs have been associated with metabolic changes that include hyperglycemia/diabetes mellitus, dyslipidemia, and weight gain. While all drugs in the class have been shown to produce some metabolic changes, each drug has its own specific risk profile.

Hyperglycemia/Diabetes Mellitus

Hyperglycemia, in some cases extreme and associated with diabetic ketoacidosis, hyperosmolar coma, or death, has been reported in patients treated with atypical antipsychotics. There have been reports of hyperglycemia in patients treated with aripiprazole [see Adverse Reactions (6.1)]. Assessment of the relationship between atypical antipsychotic use and glucose abnormalities is complicated by the possibility of an increased background risk of diabetes mellitus in patients with schizophrenia and the increasing incidence of diabetes mellitus in the general population. Given these confounders, the relationship between atypical antipsychotic use and hyperglycemia-related adverse reactions is not completely understood. However, epidemiological studies suggest an increased risk of hyperglycemia-related adverse reactions in patients treated with the atypical antipsychotics.

Patients with an established diagnosis of diabetes mellitus who are started on atypical antipsychotics should be monitored regularly for worsening of glucose control. Patients with risk factors for diabetes mellitus (e.g., obesity, family history of diabetes), who are starting treatment with atypical antipsychotics should undergo fasting blood glucose testing at the beginning of treatment and periodically during treatment. Any patient treated with atypical antipsychotics should be monitored for symptoms of hyperglycemia including polydipsia, polyuria, polyphagia, and weakness. Patients who develop symptoms of hyperglycemia during treatment with atypical antipsychotics should undergo fasting blood glucose testing. In some cases, hyperglycemia has resolved when the atypical antipsychotic was discontinued; however, some patients required continuation of anti-diabetic treatment despite discontinuation of the atypical antipsychotic drug.

In a short-term, placebo-controlled randomized trial in adults with schizophrenia, the mean change in fasting glucose was +9.8 mg/dL (N=88) in the ABILIFY MAINTENA-treated patients and +0.7 mg/dL (N=59) in the placebo-treated patients. Table 5 shows the proportion of ABILIFY MAINTENA-treated patients with normal and borderline fasting glucose at baseline and their changes in fasting glucose measurements.

Table 5: Proportion of Patients with Potential Clinically Relevant Changes in Fasting Glucose from a 12-Week Placebo-Controlled Monotherapy Trial in Adult Patients with Schizophrenia
 | Category Change (at least once) from Baseline | Treatment Arm | n/N [N = the total number of subjects who had a measurement at baseline and at least one post-baseline result. n = the number of subjects with a potentially clinically relevant shift.] | %
Fasting Glucose | Normal to High (<100 mg/dL to ≥126 mg/dL) | ABILIFY MAINTENA | 7/88 | 8.0
Fasting Glucose | Normal to High (<100 mg/dL to ≥126 mg/dL) | Placebo | 0/75 | 0.0
Fasting Glucose | Borderline to High (≥100 mg/dL and <126 mg/dL to ≥126 mg/dL) | ABILIFY MAINTENA | 1/33 | 3.0
Fasting Glucose | Borderline to High (≥100 mg/dL and <126 mg/dL to ≥126 mg/dL) | Placebo | 3/33 | 9.1

During a 52-week, open-label bipolar I disorder study in those patients who initiated ABILIFY MAINTENA treatment, 1.1% with normal baseline fasting glucose experienced a shift to high while receiving ABILIFY MAINTENA and 9.8% with borderline fasting glucose experienced a shift to high. Combined, 2.9% of these patients with normal or borderline fasting glucose experienced shifts to high fasting glucose during this trial.

Dyslipidemia

Undesirable alterations in lipids have been observed in patients treated with atypical antipsychotics.

Table 6 shows the proportion of adult patients from one short-term, placebo-controlled randomized trial in adults with schizophrenia taking ABILIFY MAINTENA, with changes in total cholesterol, fasting triglycerides, fasting LDL cholesterol and HDL cholesterol.

Table 6: Proportion of Patients with Potential Clinically Relevant Changes in Blood Lipid Parameters From a 12-Week Placebo-Controlled Monotherapy Trial in Adults with Schizophrenia
 | Treatment Arm | n/N [N = the total number of subjects who had a measurement at baseline and at least one post-baseline result. n = the number of subjects with a potentially clinically relevant shift.] | %
Total Cholesterol Normal to High (<200 mg/dL to ≥240 mg/dL) | ABILIFY MAINTENA | 3/83 | 3.6
Total Cholesterol Normal to High (<200 mg/dL to ≥240 mg/dL) | Placebo | 2/73 | 2.7
Borderline to High (200~<240 mg/dL to ≥240 mg/dL) | ABILIFY MAINTENA | 6/27 | 22.2
Borderline to High (200~<240 mg/dL to ≥240 mg/dL) | Placebo | 2/19 | 10.5
Any increase (≥40 mg/dL) | ABILIFY MAINTENA | 15/122 | 12.3
Any increase (≥40 mg/dL) | Placebo | 6/110 | 5.5
Fasting Triglycerides Normal to High (<150 mg/dL to ≥200 mg/dL) | ABILIFY MAINTENA | 7/98 | 7.1
Fasting Triglycerides Normal to High (<150 mg/dL to ≥200 mg/dL) | Placebo | 4/78 | 5.1
Borderline to High (150~<200 mg/dL to ≥200 mg/dL) | ABILIFY MAINTENA | 3/11 | 27.3
Borderline to High (150~<200 mg/dL to ≥200 mg/dL) | Placebo | 4/15 | 26.7
Any increase (≥50 mg/dL) | ABILIFY MAINTENA | 24/122 | 19.7
Any increase (≥50 mg/dL) | Placebo | 20/110 | 18.2
Fasting LDL Cholesterol Normal to High (<100 mg/dL to ≥160 mg/dL) | ABILIFY MAINTENA | 1/59 | 1.7
Fasting LDL Cholesterol Normal to High (<100 mg/dL to ≥160 mg/dL) | Placebo | 1/51 | 2.0
Borderline to High (100~<160 mg/dL to ≥160 mg/dL) | ABILIFY MAINTENA | 5/52 | 9.6
Borderline to High (100~<160 mg/dL to ≥160 mg/dL) | Placebo | 1/41 | 2.4
Any increase (≥30 mg/dL) | ABILIFY MAINTENA | 17/120 | 14.2
Any increase (≥30 mg/dL) | Placebo | 9/103 | 8.7
HDL Cholesterol Normal to Low (≥40 mg/dL to <40 mg/dL) | ABILIFY MAINTENA | 14/104 | 13.5
HDL Cholesterol Normal to Low (≥40 mg/dL to <40 mg/dL) | Placebo | 11/87 | 12.6
Any decrease (≥20 mg/dL) | ABILIFY MAINTENA | 7/122 | 5.7
Any decrease (≥20 mg/dL) | Placebo | 12/110 | 10.9

During a 52-week, open-label bipolar I disorder study in those patients who initiated ABILIFY MAINTENA, shifts from baseline in fasting cholesterol from normal to high were reported in 2.1% (total cholesterol) and 2.2% (LDL cholesterol) and shifts from baseline from normal to low were reported in 8.5% (HDL cholesterol). Of these patients with normal baseline triglycerides, 3.6% experienced shifts to high, and 0.0% experienced shifts to very high. Combined, 1.0% of these patients with normal or borderline fasting triglycerides experienced shifts to very high fasting triglycerides during this trial.

Weight Gain

Weight gain has been observed with atypical antipsychotic use. Clinical monitoring of weight is recommended.

In one short-term, placebo-controlled trial in adult patients with schizophrenia with ABILIFY MAINTENA, the mean change in body weight at Week 12 was +3.5 kg (N=99) in the ABILIFY MAINTENA-treated patients and +0.8 kg (N=66) in the placebo-treated patients.

Table 7 shows the percentage of adult patients with schizophrenia with weight gain ≥7% of body weight in a short-term, placebo-controlled trial with ABILIFY MAINTENA.

Table 7: Percentage of Patients From a 12-Week Placebo-Controlled Trial in Adult Patients with Schizophrenia with Weight Gain ≥7% of Body Weight
 | Treatment Arm | N [N = the total number of subjects who had a measurement at baseline and at least one post-baseline result.] | Patients n (%)
Weight gain ≥7% of body weight | ABILIFY MAINTENA | 144 | 31 (21.5)
Weight gain ≥7% of body weight | Placebo | 141 | 12 (8.5)

During a 52-week, open-label bipolar I disorder study in those patients who initiated ABILIFY MAINTENA, 1.8% discontinued ABILIFY MAINTENA treatment due to weight increase. ABILIFY MAINTENA was associated with mean increase from baseline in weight of 1.0 kg at week 52. In this trial, 21.4% of these patients demonstrated ≥7% increase in body weight and 15.4% demonstrated a ≥7% decrease in body weight.

5.6 Pathological Gambling and Other Compulsive Behaviors

Post-marketing case reports suggest that patients can experience intense urges, particularly for gambling, and the inability to control these urges while taking aripiprazole. Other compulsive urges, reported less frequently, include: sexual urges, shopping, eating or binge eating, and other impulsive or compulsive behaviors. Because patients may not recognize these behaviors as abnormal, it is important for prescribers to ask patients or their caregivers specifically about the development of new or intense gambling urges, compulsive sexual urges, compulsive shopping, binge or compulsive eating, or other urges while being treated with aripiprazole. It should be noted that impulse-control symptoms can be associated with the underlying disorder. In some cases, although not all, urges were reported to have stopped when the dose was reduced, or the medication was discontinued. Compulsive behaviors may result in harm to the patient and others if not recognized. Consider dose reduction or stopping the medication if a patient develops such urges.

5.7 Orthostatic Hypotension and Syncope

ABILIFY MAINTENA may cause orthostatic hypotension, perhaps due to its α1-adrenergic receptor antagonism. In the short-term, placebo-controlled trial in adults with schizophrenia, the adverse event of presyncope was reported in 1/167 (0.6%) of patients treated with ABILIFY MAINTENA, while syncope and orthostatic hypotension were each reported in 1/172 (0.6%) of patients treated with placebo. During the stabilization phase of the randomized-withdrawal (maintenance) study in adult patients with schizophrenia, orthostasis-related adverse events were reported in 4/576 (0.7%) of patients treated with ABILIFY MAINTENA, including abnormal orthostatic blood pressure (1/576, 0.2%), postural dizziness (1/576, 0.2%), presyncope (1/576, 0.2%) and orthostatic hypotension (1/576, 0.2%).

In the short-term placebo-controlled trial in adults with schizophrenia, there were no patients in either treatment group with a significant orthostatic change in blood pressure (defined as a decrease in systolic blood pressure ≥20 mmHg accompanied by an increase in heart rate ≥25 bpm when comparing standing to supine values). During the stabilization phase of the randomized-withdrawal (maintenance) study in adult patients with schizophrenia, the incidence of significant orthostatic change in blood pressure was 0.2% (1/575).

5.8 Falls

Antipsychotics, including ABILIFY MAINTENA, may cause somnolence, postural hypotension, motor and sensory instability, which may lead to falls and, consequently, fractures or other injuries. For patients with diseases, conditions, or medications that could exacerbate these effects, complete fall risk assessments when initiating antipsychotic treatment and recurrently for patients on long-term antipsychotic therapy.

5.9 Leukopenia, Neutropenia, and Agranulocytosis

In clinical trials and post-marketing experience, leukopenia and neutropenia have been reported temporally related to antipsychotic agents, including ABILIFY MAINTENA. Agranulocytosis has also been reported [see Adverse Reactions (6.1)].

Possible risk factors for leukopenia/neutropenia include pre-existing low white blood cell count (WBC)/absolute neutrophil count (ANC) and a history of drug-induced leukopenia/neutropenia. In patients with a history of a clinically significant low WBC/ANC or drug-induced leukopenia/neutropenia, perform a complete blood count (CBC) frequently during the first few months of therapy. In such patients, consider discontinuation of ABILIFY MAINTENA at the first sign of a clinically significant decline in WBC in the absence of other causative factors.

Monitor patients with clinically significant neutropenia for fever or other symptoms or signs of infection and treat promptly if such symptoms or signs occur. Discontinue ABILIFY MAINTENA in patients with severe neutropenia (absolute neutrophil count <1000/mm^3) and follow their WBC counts until recovery.

5.10 Seizures

As with other antipsychotic drugs, use ABILIFY MAINTENA cautiously in patients with a history of seizures or with conditions that lower the seizure threshold. Conditions that lower the seizure threshold may be more prevalent in a population of 65 years or older.

5.11 Potential for Cognitive and Motor Impairment

ABILIFY MAINTENA, like other antipsychotics, may impair judgment, thinking, or motor skills. Patients should be cautioned about performing activities that require mental alertness such as operating hazardous machinery, or operating a motor vehicle, until they are reasonably certain that therapy with ABILIFY MAINTENA does not affect them adversely.

5.12 Body Temperature Regulation

Disruption of the body's ability to reduce core body temperature has been attributed to antipsychotic agents. Appropriate care is advised when prescribing ABILIFY MAINTENA for patients who will be experiencing conditions which may contribute to an elevation in core body temperature, (e.g., exercising strenuously, exposure to extreme heat, receiving concomitant medication with anticholinergic activity, or being subject to dehydration).

5.13 Dysphagia

Esophageal dysmotility and aspiration have been associated with antipsychotic drug use, including ABILIFY MAINTENA. ABILIFY MAINTENA and other antipsychotic drugs should be used cautiously in patients at risk for aspiration pneumonia [see Warnings and Precautions (5.1)].

6 ADVERSE REACTIONS

The following adverse reactions are discussed in more detail in other sections of the labeling:

- Increased Mortality in Elderly Patients with Dementia - Related Psychosis Use [see Boxed Warning and Warnings and Precautions (5.1)]
- Cerebrovascular Adverse Reactions, Including Stroke in Elderly Patients with Dementia-Related Psychosis [see Boxed Warning and Warnings and Precautions (5.2)]
- Neuroleptic Malignant Syndrome [see Warnings and Precautions (5.3)]
- Tardive Dyskinesia [see Warnings and Precautions (5.4)]
- Metabolic Changes [see Warnings and Precautions (5.5)]
- Pathological Gambling and Other Compulsive Behaviors [see Warnings and Precautions (5.6)]
- Orthostatic Hypotension and Syncope [see Warnings and Precautions (5.7)]
- Falls [see Warnings and Precautions (5.8)]
- Leukopenia, Neutropenia, and Agranulocytosis [see Warnings and Precautions (5.9)]
- Seizures [see Warnings and Precautions (5.10)]
- Potential for Cognitive and Motor Impairment [see Warnings and Precautions (5.11)]
- Body Temperature Regulation [see Warnings and Precautions (5.12)]
- Dysphagia [see Warnings and Precautions (5.13)]

6.1 Clinical Trials Experience

Because clinical trials are conducted under widely varying conditions, adverse reaction rates observed in the clinical trials of a drug cannot be directly compared to rates in the clinical trials of another drug and may not reflect the rates observed in practice.

Safety Database of ABILIFY MAINTENA and Oral Aripiprazole

Oral aripiprazole has been evaluated for safety in 16,114 adult patients who participated in multiple-dose, clinical trials in schizophrenia and other indications, and who had approximately 8,578 patient-years of exposure to oral aripiprazole. A total of 3,901 patients were treated with oral aripiprazole for at least 180 days, 2,259 patients were treated with oral aripiprazole for at least 360 days, and 933 patients continuing aripiprazole treatment for at least 720 days.

ABILIFY MAINTENA has been evaluated for safety in 2,128 adult patients in clinical trials in schizophrenia, with approximately 2,633 patient-years of exposure to ABILIFY MAINTENA. A total of 1,229 patients were treated with ABILIFY MAINTENA for at least 180 days (at least 7 consecutive injections) and 935 patients treated with ABILIFY MAINTENA had at least 1 year of exposure (at least 13 consecutive injections).

ABILIFY MAINTENA has been evaluated for safety in 804 adult patients in clinical trials in bipolar I disorder, with approximately 530 patient-years of exposure to ABILIFY MAINTENA. A total of 419 patients were treated with ABILIFY MAINTENA for at least 180 days (at least 7 consecutive injections) and 287 patients treated with ABILIFY MAINTENA had at least 1 year of exposure (at least 13 consecutive injections).

The conditions and duration of treatment with ABILIFY MAINTENA included double-blind and open-label studies. The safety data presented below are derived from the 12-week double-blind placebo-controlled study of ABILIFY MAINTENA in adult patients with schizophrenia.

Adverse Reactions with ABILIFY MAINTENA

Most Commonly Observed Adverse Reactions in Double-Blind, Placebo-Controlled Clinical Trials in Schizophrenia

Based on the placebo-controlled trial of ABILIFY MAINTENA in schizophrenia, the most commonly observed adverse reactions associated with the use of ABILIFY MAINTENA in patients (incidence of 5% or greater and aripiprazole incidence at least twice that for placebo) were increased weight (16.8% vs. 7.0%), akathisia (11.4% vs. 3.5%), injection site pain (5.4% vs. 0.6%) and sedation (5.4% vs. 1.2%).

Commonly Reported Adverse Reactions in Double-Blind, Placebo-Controlled Clinical Trials in Schizophrenia

The following findings are based on the double-blind, placebo-controlled trial that compared ABILIFY MAINTENA 400 mg or 300 mg to placebo in patients with schizophrenia. Table 8 lists the adverse reactions reported in 2% or more of ABILIFY MAINTENA-treated subjects and at a greater proportion than in the placebo group.

Table 8: Adverse Reactions in ≥2% of ABILIFY MAINTENA-Treated Adult Patients with Schizophrenia in a 12-Week Double-Blind, Placebo-Controlled Trial [This table does not include adverse reactions which had an incidence equal to or less than placebo.]
 | Percentage of Patients Reporting Reaction
 | ABILIFY MAINTENA | Placebo
Preferred Term | (n=167) | (n=172)
Gastrointestinal Disorders
Constipation | 10 | 7
Dry Mouth | 4 | 2
Diarrhea | 3 | 2
Vomiting | 3 | 1
Abdominal Discomfort | 2 | 1
General Disorders and Administration Site Conditions
Injection Site Pain | 5 | 1
Infections and Infestations
Upper Respiratory Tract Infection | 4 | 2
Investigations
Increased Weight | 17 | 7
Decreased Weight | 4 | 2
Musculoskeletal and Connective Tissue Disorders
Arthralgia | 4 | 1
Back Pain | 4 | 2
Myalgia | 4 | 2
Musculoskeletal Pain | 3 | 1
Nervous System Disorders
Akathisia | 11 | 4
Sedation | 5 | 1
Dizziness | 4 | 2
Tremor | 3 | 1
Respiratory, Thoracic and Mediastinal
Nasal Congestion | 2 | 1

Other Adverse Reactions Observed During the Clinical Trial Evaluation of ABILIFY MAINTENA

The following listing does not include reactions: 1) already listed in previous tables or elsewhere in labeling, 2) for which a drug cause was remote, 3) which were so general as to be uninformative, 4) which were not considered to have significant clinical implications, or 5) which occurred at a rate equal to or less than placebo.

Reactions are categorized by body system according to the following definitions: frequent adverse reactions are those occurring in at least 1/100 patients; infrequent adverse reactions are those occurring in 1/100 to 1/1000 patients; rare reactions are those occurring in fewer than 1/1000 patients:

- Blood and Lymphatic System Disorders: rare - thrombocytopenia
- Cardiac Disorders: infrequent - tachycardia; rare - bradycardia, sinus tachycardia
- Endocrine Disorders: rare - hypoprolactinemia
- Eye Disorders: infrequent - vision blurred, oculogyric crisis
- Gastrointestinal Disorders: infrequent - abdominal pain upper, dyspepsia, nausea; rare -swollen tongue
- General Disorders and Administration Site Conditions: frequent - fatigue, injection site reactions (including erythema, induration, pruritus, injection site reaction, swelling, rash, inflammation, hemorrhage); infrequent - chest discomfort, gait disturbance; rare -irritability, pyrexia
- Hepatobiliary Disorders: rare - drug induced liver injury
- Immune System Disorders: rare - drug hypersensitivity
- Infections and Infestations: rare - nasopharyngitis
- Investigations: infrequent - blood creatine phosphokinase increased, blood pressure decreased, hepatic enzyme increased, liver function test abnormal, electrocardiogram QT-prolonged; rare - blood triglycerides decreased, blood cholesterol decreased, electrocardiogram T-wave abnormal
- Metabolism and Nutrition Disorders: infrequent - decreased appetite, obesity, hyperinsulinemia
- Musculoskeletal and Connective Tissue Disorders: infrequent - joint stiffness, muscle twitching, trismus; rare - rhabdomyolysis
- Nervous System Disorders: infrequent - extrapyramidal disorder, hypersomnia, lethargy; rare - bradykinesia, convulsion, dysgeusia, memory impairment, oromandibular dystonia
- Psychiatric Disorders: frequent - anxiety, insomnia, restlessness; infrequent - agitation, bruxism, psychotic disorder, suicidal ideation; rare - aggression, hypersexuality, panic attack
- Renal and Urinary Disorders: rare - glycosuria, pollakiuria, urinary incontinence
- Reproductive System and Breast Disorders: infrequent - ejaculation delayed
- Vascular Disorders: infrequent - hypertension

Demographic Differences

An examination of population subgroups was performed across demographic subgroup categories for adverse reactions experienced by at least 5% of ABILIFY MAINTENA subjects at least twice rate of the placebo (i.e., increased weight, akathisia, injection site pain, and sedation) in the double-blind placebo-controlled trial. This analysis did not reveal evidence of differences in safety differential adverse reaction incidence on the basis of age, gender, or race alone; however, there were few subjects ≥65 years of age.

Injection Site Reactions of ABILIFY MAINTENA

In the data from the short-term, double-blind, placebo-controlled trial with ABILIFY MAINTENA in patients with schizophrenia, the percent of patients reporting any injection site-related adverse reaction (all reported as injection site pain) was 5.4% for patients treated with gluteal administered ABILIFY MAINTENA and 0.6% for placebo. The mean intensity of injection pain reported by subjects using a visual analog scale (0=no pain to 100=unbearably painful) approximately one hour after injection was 7.1 (SD 14.5) for the first injection and 4.8 (SD 12.4) at the last visit in the double-blind, placebo-controlled phase.

In an open-label study comparing bioavailability of ABILIFY MAINTENA administered in the deltoid or gluteal muscle, injection site pain was observed in both groups at approximately equal rates.

Extrapyramidal Symptoms (EPS)

In the short-term, placebo-controlled trial of ABILIFY MAINTENA in adults with schizophrenia, the incidence of reported EPS-related events, excluding events related to akathisia, for ABILIFY MAINTENA-treated patients was 9.6% vs. 5.2% for placebo. The incidence of akathisia-related events for ABILIFY MAINTENA-treated patients was 11.5% vs. 3.5% for placebo.

Dystonia

Symptoms of dystonia, prolonged abnormal contractions of muscle groups, may occur in susceptible individuals during the first few days of treatment. Dystonic symptoms include: spasm of the neck muscles, sometimes progressing to tightness of the throat, swallowing difficulty, difficulty breathing, and/or protrusion of the tongue. While these symptoms can occur at low doses, they occur more frequently and with greater severity with high potency and at higher doses of first-generation antipsychotic drugs. An elevated risk of acute dystonia is observed in males and younger age groups. In the short-term, placebo-controlled trial of ABILIFY MAINTENA in adults with schizophrenia, the incidence of dystonia was 1.8% for ABILIFY MAINTENA vs. 0.6% for placebo.

Neutropenia

In the short-term, placebo-controlled trial of ABILIFY MAINTENA in adults with schizophrenia, the incidence of neutropenia (absolute neutrophil count ≤1.5 thous/mcL) for ABILIFY MAINTENA-treated patients was 5.7% vs. 2.1% for placebo. An absolute neutrophil count of <1 thous/mcL (i.e., 0.95 thous/mcL) was observed in only one patient on ABILIFY MAINTENA and resolved spontaneously without any associated adverse events [see Warnings and Precautions (5.9)].

Adverse Reactions Reported in Clinical Trials with Oral Aripiprazole

The following is a list of additional adverse reactions that have been reported in clinical trials with oral aripiprazole and not reported above for ABILIFY MAINTENA:

- Cardiac Disorders: palpitations, cardiopulmonary failure, myocardial infarction, cardio-respiratory arrest, atrioventricular block, extrasystoles, angina pectoris, myocardial ischemia, atrial flutter, supraventricular tachycardia, ventricular tachycardia
- Eye Disorders: photophobia, diplopia, eyelid edema, photopsia
- Gastrointestinal Disorders: gastroesophageal reflux disease, swollen tongue, esophagitis, pancreatitis, stomach discomfort, toothache
- General Disorders and Administration Site Conditions: asthenia, peripheral edema, chest pain, face edema, angioedema, hypothermia, pain
- Hepatobiliary Disorders: hepatitis, jaundice
- Immune System Disorders: hypersensitivity
- Injury, Poisoning, and Procedural Complications: heat stroke
- Investigations: blood prolactin decreased, blood prolactin increased, blood urea increased, blood creatinine increased, blood bilirubin increased, blood lactate dehydrogenase increased, glycosylated hemoglobin increased
- Metabolism and Nutrition Disorders: anorexia, hyponatremia, hypoglycemia, polydipsia, diabetic ketoacidosis
- Musculoskeletal and Connective Tissue Disorders: muscle rigidity, muscular weakness, muscle tightness, decreased mobility, rhabdomyolysis, musculoskeletal stiffness, pain in extremity, muscle spasms
- Nervous System Disorders: coordination abnormal, speech disorder, hypokinesia, hypotonia, myoclonus, akinesia, bradykinesia, choreoathetosis
- Psychiatric Disorders: loss of libido, suicide attempt, hostility, libido increased, anger, anorgasmia, delirium, intentional self-injury, completed suicide, tic, homicidal ideation, catatonia, sleepwalking
- Renal and Urinary Disorders: urinary retention, polyuria, nocturia
- Reproductive System and Breast Disorders: menstruation irregular, erectile dysfunction, amenorrhea, breast pain, gynecomastia, priapism
- Respiratory, Thoracic, and Mediastinal Disorders: nasal congestion, dyspnea, pharyngolaryngeal pain, cough
- Skin and Subcutaneous Tissue Disorders: rash (including erythematous, exfoliative, generalized, macular, maculopapular, papular rash; acneiform, allergic, contact, exfoliative, seborrheic dermatitis, neurodermatitis, and drug eruption), hyperhidrosis, pruritus, photosensitivity reaction, alopecia, urticaria

6.2 Postmarketing Experience

The following adverse reactions have been identified during post-approval use of oral aripiprazole or ABILIFY MAINTENA. Because these reactions are reported voluntarily from a population of uncertain size, it is not always possible to reliably estimate their frequency or establish a causal relationship to drug exposure: occurrences of allergic reaction (anaphylactic reaction, angioedema, laryngospasm, pruritus/urticaria, or oropharyngeal spasm), pathological gambling, hiccups, blood glucose fluctuation, drug reaction with eosinophilia and systemic symptoms (DRESS), and fecal incontinence.

7 DRUG INTERACTIONS

7.1 Drugs Having Clinically Important Interactions with ABILIFY MAINTENA

Table 9: Clinically Important Drug Interactions with ABILIFY MAINTENA:
Concomitant Drug Name or Drug Class | Clinical Rationale | Clinical Recommendation
Strong CYP3A4 Inhibitors (e.g., ketoconazole) or strong CYP2D6 inhibitors (e.g., paroxetine, fluoxetine) | The concomitant use of oral aripiprazole with strong CYP3A4 or CYP2D6 inhibitors increased the exposure of aripiprazole [see Clinical Pharmacology (12.3)]. | With concomitant use of ABILIFY MAINTENA with a strong CYP3A4 inhibitor or CYP2D6 inhibitor for more than 14 days, reduce the ABILIFY MAINTENA dosage [see Dosage and Administration (2.4)].
Strong CYP3A4 Inducers (e.g., carbamazepine) | The concomitant use of oral aripiprazole and carbamazepine decreased the exposure of aripiprazole [see Clinical Pharmacology (12.3)]. | Avoid use of ABILIFY MAINTENA in combination with carbamazepine and other inducers of CYP3A4 for greater than 14 days [see Dosage and Administration (2.4)].
Antihypertensive Drugs | Due to its alpha-adrenergic antagonism, aripiprazole has the potential to enhance the effect of certain antihypertensive agents. | Monitor blood pressure and adjust dose accordingly [see Warnings and Precautions (5.7)].
Benzodiazepines (e.g., lorazepam) | The intensity of sedation was greater with the combination of oral aripiprazole and lorazepam as compared to that observed with aripiprazole alone. The orthostatic hypotension observed was greater with the combination as compared to that observed with lorazepam alone [see Warnings and Precautions (5.7)]. | Monitor sedation and blood pressure. Adjust dose accordingly.

7.2 Drugs Having No Clinically Important Interactions with ABILIFY MAINTENA

Based on pharmacokinetic studies with oral aripiprazole, no dosage adjustment of ABILIFY MAINTENA is required when administered concomitantly with famotidine, valproate, lithium, lorazepam [see Clinical Pharmacology (12.3)].

In addition, no dosage adjustment is necessary for substrates of CYP2D6 (e.g., dextromethorphan, fluoxetine, paroxetine, or venlafaxine), CYP2C9 (e.g., warfarin), CYP2C19 (e.g., omeprazole, warfarin), or CYP3A4 (e.g., dextromethorphan) when coadministered with ABILIFY MAINTENA. Additionally, no dosage adjustment is necessary for valproate, lithium, lamotrigine, lorazepam, or sertraline when coadministered with ABILIFY MAINTENA. [See Clinical Pharmacology (12.3)].

8 USE IN SPECIFIC POPULATIONS

8.1 Pregnancy

Pregnancy Exposure Registry

There is a pregnancy exposure registry that monitors pregnancy outcomes in women exposed to ABILIFY MAINTENA during pregnancy. For more information contact the National Pregnancy Registry for Atypical Antipsychotics at 1-866-961-2388 or visit http://womensmentalhealth.org/clinical-and-research-programs/pregnancyregistry/.

Risk Summary

Neonates exposed to antipsychotic drugs, including ABILIFY MAINTENA, during the third trimester of pregnancy are at risk for extrapyramidal and/or withdrawal symptoms following delivery (see Clinical Considerations). Overall available data from published epidemiologic studies of pregnant women exposed to aripiprazole have not established a drug-associated risk of major birth defects, miscarriage, or adverse maternal outcomes. There are risks to the mother associated with untreated schizophrenia or bipolar I disorder and with exposure to antipsychotics, including ABILIFY MAINTENA, during pregnancy (see Clinical Considerations). Aripiprazole exposure during pregnancy may decrease milk supply in the post-partum period [see Use in Specific Populations (8.2)].

In animal reproduction studies, oral and intravenous aripiprazole administration during organogenesis in rats and/or rabbits at doses 10 and 11 times, respectively, the maximum recommended human dose (MRHD) produced fetal death, decreased fetal weight, undescended testicles, delayed skeletal ossification, skeletal abnormalities, and diaphragmatic hernia. Oral and intravenous aripiprazole administration during the pre- and post-natal period in rats at doses 10 times the MRHD produced prolonged gestation, stillbirths, decreased pup weight, and decreased pup survival (see Data).

The background risk of major birth defects and miscarriage for the indicated population are unknown. All pregnancies have a background risk of birth defect, loss, or other adverse outcomes. In the U.S. general population, the estimated background risk of major birth defects and miscarriage in clinically recognized pregnancies is 2 to 4% and 15 to 20%, respectively.

Clinical Considerations

Disease-associated maternal and/or embryo/fetal risk

There is a risk to the mother from untreated schizophrenia or bipolar I disorder, including increased risk of relapse, hospitalization, and suicide. Schizophrenia and bipolar I disorder are associated with increased adverse perinatal outcomes, including preterm birth. It is not known if this is a direct result of the illness or other comorbid factors.

Fetal/Neonatal Adverse Reactions

Extrapyramidal and/or withdrawal symptoms, including agitation, hypertonia, hypotonia, tremor, somnolence, respiratory distress and feeding disorder have been reported in neonates who were exposed to antipsychotic drugs (including oral aripiprazole) during the third trimester of pregnancy. These symptoms have varied in severity. Some neonates recovered within hours or days without specific treatment; others required prolonged hospitalization. Monitor neonates exhibiting extrapyramidal and/or withdrawal symptoms and manage symptoms appropriately.

Data

Animal Data

In animal studies, aripiprazole demonstrated developmental toxicity, including possible teratogenic effects in rats and rabbits.

Pregnant rats were treated with oral doses of 3, 10, and 30 mg/kg/day which are approximately 1 to 10 times the MRHD of 30 mg/day on a mg/m^2 basis of aripiprazole during the period of organogenesis. Treatment at the highest dose caused a slight prolongation of gestation and delay in fetal development, as evidenced by decreased fetal weight and undescended testes. Delayed skeletal ossification was observed at 3 and 10 times the oral MRHD on mg/m^2 basis.

At 3 and 10 times the oral MRHD on a mg/m^2 basis, delivered offspring had decreased body weights. Increased incidences of hepatodiaphragmatic nodules and diaphragmatic hernia were observed in offspring from the highest dose group (the other dose groups were not examined for these findings). Postnatally, delayed vaginal opening was seen at 3 and 10 times the oral MRHD on a mg/m^2 basis and impaired reproductive performance (decreased fertility rate, corpora lutea, implants, live fetuses, and increased post-implantation loss, likely mediated through effects on female offspring) along with some maternal toxicity were seen at the highest dose; however, there was no evidence to suggest that these developmental effects were secondary to maternal toxicity.

In pregnant rats treated with aripiprazole intravenously at doses of 3, 9, and 27 mg/kg/day, which are 1 to 9 times the oral MRHD on mg/m^2 basis, during the period of organogenesis, decreased fetal weight and delayed skeletal ossification were seen at the highest dose which also caused maternal toxicity.

In pregnant rabbits treated with oral doses of 10, 30, and 100 mg/kg/day which are 2 to 11 times human exposure at the oral MRHD based on AUC and 6 to 65 times the oral MRHD of aripiprazole on mg/m^2 basis during the period of organogenesis, decreased maternal food consumption and increased abortions were seen at the highest dose as well as increased fetal mortality. Decreased fetal weight and increased incidence of fused sternebrae were observed at 3 and 11 times the MRHD based on AUC.

In pregnant rabbits receiving aripiprazole injection intravenously at doses of 3, 10, and 30 mg/kg/day, which are 2 to 19 times the oral MRHD on mg/m^2 basis during the period of organogenesis, the highest dose caused pronounced maternal toxicity that resulted in decreased fetal weight, increased fetal abnormalities (primarily skeletal), and decreased fetal skeletal ossification. The fetal no-effect dose was 5 times the human exposure at the oral MRHD based on AUC and is 6 times the oral MRHD on mg/m^2 basis.

In rats treated with oral doses of 3, 10, and 30 mg/kg/day, which are 1 to 10 times the oral MRHD of aripiprazole on a mg/m^2 basis, peri- and post-natally (from Day 17 of gestation through Day 21 postpartum), slight maternal toxicity and slightly prolonged gestation were seen at the highest dose. An increase in stillbirths and decreases in pup weight (persisting into adulthood) and survival were also seen at this dose.

In rats treated with aripiprazole intravenously at doses of 3, 8, and 20 mg/kg/day which are 1 to 6 times the oral MRHD on mg/m^2 basis from Day 6 of gestation through Day 20 postpartum, increased stillbirths were seen at 3 and 6 times the MRHD on mg/m^2 basis, and decreases in early postnatal pup weight and survival were seen at the highest dose; these doses produced some maternal toxicity. There were no effects on postnatal behavioral and reproductive development.

8.2 Lactation

Risk Summary

Aripiprazole is present in human breast milk. Based on published case reports and pharmacovigilance reports, aripiprazole exposure during pregnancy and/or the postpartum period may lead to clinically relevant decreases in milk supply which may be reversible with discontinuation of the drug. There are also reports of aripiprazole exposure during pregnancy and no maternal milk supply in the post-partum period. Effects on milk supply may be mediated through decreases in prolactin levels, which have been observed [see Adverse Reactions (6.1)]. Monitor the breastfed infant for dehydration and lack of appropriate weight gain. The developmental and health benefits of breastfeeding should be considered along with the mother's clinical need for ABILIFY MAINTENA and any potential adverse effects on the breastfed infant from ABILIFY MAINTENA or from the underlying maternal condition.

8.4 Pediatric Use

ABILIFY MAINTENA has not been studied in children 18 years of age or younger. However, juvenile animal studies have been conducted in rats and dogs.

Juvenile Animal Studies

Aripiprazole in juvenile rats caused mortality, CNS clinical signs, impaired memory and learning, and delayed sexual maturation when administered at oral doses of 10, 20, 40 mg/kg/day from weaning (21 days old) through maturity (80 days old). At 40 mg/kg/day, mortality, decreased activity, splayed hind limbs, hunched posture, ataxia, tremors and other CNS signs were observed in both genders. In addition, delayed sexual maturation was observed in males. At all doses and in a dose-dependent manner, impaired memory and learning, increased motor activity, and histopathology changes in the pituitary (atrophy), adrenals (adrenocortical hypertrophy), mammary glands (hyperplasia and increased secretion), and female reproductive organs (vaginal mucification, endometrial atrophy, decrease in ovarian corpora lutea) were observed. The changes in female reproductive organs were considered secondary to the increase in prolactin serum levels. A No Observed Adverse Effect Level (NOAEL) could not be determined and, at the lowest tested dose of 10 mg/kg/day, there is no safety margin relative to the systemic exposures (AUC0-24) for aripiprazole or its major active metabolite in adolescents at the maximum recommended pediatric dose of 15 mg/day. All drug-related effects were reversible after a 2-month recovery period, and most of the drug effects in juvenile rats were also observed in adult rats from previously conducted studies.

Aripiprazole in juvenile dogs (2 months old) caused CNS clinical signs of tremors, hypoactivity, ataxia, recumbency and limited use of hind limbs when administered orally for 6 months at 3, 10, 30 mg/kg/day. Mean body weight and weight gain were decreased up to 18% in females in all drug groups relative to control values. A NOAEL could not be determined and, at the lowest tested dose of 3 mg/kg/day, there is no safety margin relative to the systemic exposures (AUC0-24) for aripiprazole or its major active metabolite in adolescents at the maximum recommended pediatric dose of 15 mg/day. All drug-related effects were reversible after a 2-month recovery period.

8.5 Geriatric Use

Clinical studies of oral aripiprazole did not include sufficient numbers of subjects aged 65 years and over to determine whether they respond differently from younger subjects. Other reported clinical experience and pharmacokinetic data have not identified differences in responses between the elderly and younger patients [see Clinical Pharmacology (12.3)]. In general, dose selection for an elderly patient should be cautious, usually starting at the low end of the dosing range, reflecting the greater frequency of decreased hepatic, renal, or cardiac function, and of concomitant disease or other drug therapy.

In single-dose and multiple-dose pharmacokinetic studies, there was no detectable age effect in the population pharmacokinetic analysis of oral aripiprazole in schizophrenia patients [see Clinical Pharmacology (12.3)]. No dosage adjustments are recommended based on age alone. ABILIFY MAINTENA is not approved for the treatment of patients with dementia-related psychosis [see also Boxed Warning and Warnings and Precautions (5.1)].

8.6 CYP2D6 Poor Metabolizers

Dosage adjustment is recommended in known CYP2D6 poor metabolizers due to high aripiprazole concentrations. Approximately 8% of Caucasians and 3% to 8% of Black/African Americans cannot metabolize CYP2D6 substrates and are classified as poor metabolizers (PM) [see Dosage and Administration (2.4)].

10 OVERDOSAGE

Human Experience

The largest known case of acute ingestion with a known outcome involved 1260 mg of oral aripiprazole (42 times the maximum recommended daily dose) in a patient who fully recovered.

Common adverse reactions (reported in at least 5% of all overdose cases) reported with oral aripiprazole overdosage (alone or in combination with other substances) include vomiting, somnolence, and tremor. Other clinically important signs and symptoms observed in one or more patients with aripiprazole overdoses (alone or with other substances) include acidosis, aggression, aspartate aminotransferase increased, atrial fibrillation, bradycardia, coma, confusional state, convulsion, blood creatine phosphokinase increased, depressed level of consciousness, hypertension, hypokalemia, hypotension, lethargy, loss of consciousness, QRS complex prolonged, QT prolonged, pneumonia aspiration, respiratory arrest, status epilepticus, and tachycardia.

Management of Overdosage

In case of overdosage, call the Poison Control Center immediately at 1-800-222-1222.

11 DESCRIPTION

Aripiprazole is an atypical antipsychotic which is present in ABILIFY MAINTENA as its monohydrate polymorphic form. Aripiprazole monohydrate is 7-[4-[4-(2,3-dichlorophenyl)-1-piperazinyl] butoxy]-3,4 dihydrocarbostyril monohydrate. The empirical formula is C23H27Cl2N3O2∙H2O and its molecular weight is 466.40. The chemical structure is:

ABILIFY MAINTENA (aripiprazole) is an extended-release injectable suspension available in 400 mg or 300 mg strength pre-filled dual chamber syringes and 400 mg or 300 mg strength vials. The labeled strengths are calculated based on the anhydrous form (aripiprazole). Inactive ingredients (per administered dose) for 400 mg and 300 mg strength products, respectively, include carboxymethyl cellulose sodium (16.64 mg and 12.48 mg), mannitol (83.2 mg and 62.4 mg), sodium phosphate monobasic monohydrate (1.48 mg and 1.11 mg) and sodium hydroxide (pH adjuster).

12 CLINICAL PHARMACOLOGY

12.1 Mechanism of Action

The mechanism of action of aripiprazole in the treatment of schizophrenia and bipolar I disorder is unknown.

The efficacy of aripiprazole could be mediated through a combination of partial agonist activity at dopamine D2 and serotonin 5-HT1A receptors and antagonist activity at 5-HT2A receptors.

12.2 Pharmacodynamics

Aripiprazole exhibits high affinity for dopamine D2 and D3 (Kis 0.34 and 0.8 nM, respectively), serotonin 5-HT1A and 5-HT2A receptors (Kis 1.7 and 3.4 nM, respectively), moderate affinity for dopamine D4, serotonin 5-HT2C and 5-HT7, alpha1-adrenergic and histamine H1 receptors (Kis of 44 nM, 15 nM, 39 nM, 57 nM, and 61 nM, respectively), and moderate affinity for the serotonin reuptake site (Ki=98 nM). Aripiprazole has no appreciable affinity for cholinergic muscarinic receptors (IC50>1000 nM). Actions at receptors other than D2, 5-HT1A, and 5-HT2A could explain some of the other adverse reactions of aripiprazole (e.g., the orthostatic hypotension observed with aripiprazole may be explained by its antagonist activity at adrenergic alpha1 receptors).

Alcohol

There was no significant difference between oral aripiprazole coadministered with ethanol and placebo coadministered with ethanol on performance of gross motor skills or stimulus response in healthy subjects. As with most psychoactive medications, patients should be advised to avoid alcohol while taking ABILIFY MAINTENA.

ABILIFY MAINTENA activity is presumably primarily due to the parent drug, aripiprazole, and to a lesser extent, to its major metabolite, dehydro-aripiprazole, which has been shown to have affinities for D2 receptors similar to the parent drug.

12.3 Pharmacokinetics

Steady-state concentrations for the typical subject were attained by the fourth dose for both sites of administration. Approximate dose-proportional increases in aripiprazole and dehydro-aripiprazole exposure were observed after every four-week ABILIFY MAINTENA injections of 300 mg and 400 mg.

Absorption

Aripiprazole absorption into the systemic circulation is slow and prolonged following intramuscular injection due to low solubility of aripiprazole particles. Following a single-dose administration of ABILIFY MAINTENA in the deltoid and gluteal muscle, the extent of absorption (AUCtau, AUCinf) of aripiprazole was similar for both injection sites, but the rate of absorption (Cmax) was 31% higher following administration to the deltoid compared to the gluteal site. However, at steady state, AUCtau and Cmax were similar for both sites of injection. Following multiple intramuscular doses, the plasma concentrations of aripiprazole gradually rise to maximum plasma concentrations at a median Tmax of 5 to 7 days for the gluteal muscle and 4 days for the deltoid muscle.

Distribution

Based on results from trials with oral administration of aripiprazole, aripiprazole is widely distributed throughout the body with an apparent volume of distribution of 4.9 L/kg, indicating extensive extravascular distribution. At therapeutic concentrations, aripiprazole and dehydro-aripiprazole are greater than 99% bound to serum proteins, binding primarily to albumin.

Elimination

Following single dose administration of ABILIFY MAINTENA, the mean apparent terminal elimination half-life of aripiprazole was 17.8 and 21 days, for deltoid and gluteal injections, respectively.

After multiple gluteal administrations, the mean apparent terminal elimination half-life of aripiprazole was 29.9 days and 46.5 days for every 4-week injection of ABILIFY MAINTENA 300 mg and 400 mg, respectively.

Metabolism

Aripiprazole is metabolized primarily by three biotransformation pathways: dehydrogenation, hydroxylation, and N-dealkylation. Based on in vitro studies, CYP3A4 and CYP2D6 enzymes are responsible for dehydrogenation and hydroxylation of aripiprazole, and N-dealkylation is catalyzed by CYP3A4. Aripiprazole is the predominant drug moiety in the systemic circulation. Dehydro aripiprazole represents about 29% of the parent drug AUC in plasma.

Excretion

Following a single oral dose of [14C]-labeled aripiprazole, approximately 25% and 55% of the administered radioactivity was recovered in the urine and feces, respectively. Less than 1% of unchanged aripiprazole was excreted in the urine and approximately 18% of the oral dose was recovered unchanged in the feces.

Studies in Specific Populations

No specific pharmacokinetic studies have been performed with ABILIFY MAINTENA in specific populations. All the information is obtained from studies with oral aripiprazole.

Exposures of aripiprazole and dehydro-aripiprazole in specific populations are summarized in Figure 19 and Figure 20, respectively. In addition, in pediatric patients (10 to 17 years of age) administered with oral aripiprazole (20 mg to 30 mg), the body weight corrected aripiprazole clearance was similar to the adults.

Figure 19: Effects of intrinsic factors on aripiprazole pharmacokinetics

Figure 20: Effects of intrinsic factors on dehydro-aripiprazole pharmacokinetics:

Drug Interaction Studies

No specific drug interaction studies have been performed with ABILIFY MAINTENA. The information below is obtained from studies with oral aripiprazole.

Effects of other drugs on the exposures of aripiprazole and dehydro-aripiprazole are summarized in Figure 21 and Figure 22, respectively. Based on simulation, a 4.5-fold increase in mean Cmax and AUC values at steady-state is expected when extensive metabolizers of CYP2D6 are administered with both strong CYP2D6 and CYP3A4 inhibitors. After oral administration, a 3-fold increase in mean Cmax and AUC values at steady-state is expected in poor metabolizers of CYP2D6 administered with strong CYP3A4 inhibitors.

Figure 21: The effects of other drugs on aripiprazole pharmacokinetics

Figure 22: The effects of other drugs on dehydro-aripiprazole pharmacokinetics

The effects of oral aripiprazole on the exposures of other drugs are summarized in Figure 23. A population PK analysis in patients with major depressive disorder showed no substantial change in plasma concentrations of fluoxetine (20 mg/day or 40 mg/day), paroxetine CR (37.5 mg/day or 50 mg/day), or sertraline (100 mg/day or 150 mg/day) dosed to steady-state. The steady-state plasma concentrations of fluoxetine and norfluoxetine increased by about 18% and 36%, respectively, and concentrations of paroxetine decreased by about 27%. The steady-state plasma concentrations of sertraline and desmethylsertraline were not substantially changed when these antidepressant therapies were coadministered with aripiprazole.

Figure 23: The effects of oral aripiprazole on pharmacokinetics of other drugs

In vitro

Aripiprazole is not a substrate of CYP1A1, CYP1A2, CYP2A6, CYP2B6, CYP2C8, CYP2C9, CYP2C19, or CYP2E1 enzymes. Aripiprazole also does not undergo direct glucuronidation.

13 NONCLINICAL TOXICOLOGY

13.1 Carcinogenesis, Mutagenesis, Impairment of Fertility

Carcinogenesis

Lifetime carcinogenicity studies were conducted in ICR mice, Sprague-Dawley (SD) rats, and F344 rats. Aripiprazole was administered for 2 years in the diet at doses of 1, 3, 10, and 30 mg/kg/day to ICR mice and 1, 3, and 10 mg/kg/day to F344 rats (0.2 to 5 times and 0.3 to 3 times the maximum recommended human dose [MRHD] based on mg/m^2, respectively). In addition, SD rats were dosed orally for 2 years at 10, 20, 40, and 60 mg/kg/day (3 to 19 times the MRHD based on mg/m^2). Aripiprazole did not induce tumors in male mice or male rats. In female mice, the incidences of pituitary gland adenomas and mammary gland adenocarcinomas and adenoacanthomas were increased at dietary doses of 3 to 30 mg/kg/day (0.1 to 0.9 times human exposure at MRHD based on AUC and 0.5 to 5 times the MRHD based on mg/m^2). In female rats, the incidence of mammary gland fibroadenomas was increased at a dietary dose of 10 mg/kg/day (0.1 times human exposure at MRHD based on AUC and 3 times the MRHD based on mg/m^2); and the incidences of adrenocortical carcinomas and combined adrenocortical adenomas/carcinomas were increased at an oral dose of 60 mg/kg/day (14 times human exposure at MRHD based on AUC and 19 times the MRHD based on mg/m^2).

Proliferative changes in the pituitary and mammary gland of rodents have been observed following chronic administration of other antipsychotic agents and are considered prolactin-mediated. Serum prolactin was not measured in the aripiprazole carcinogenicity studies. However, increases in serum prolactin levels were observed in female mice in a 13-week dietary study at the doses associated with mammary gland and pituitary tumors. Serum prolactin was not increased in female rats in 4-week and 13-week dietary studies at the dose associated with mammary gland tumors. The relevance for human risk of the findings of prolactin-mediated endocrine tumors in rodents is unknown.

Mutagenesis

The mutagenic potential of aripiprazole was tested in the in vitro bacterial reverse-mutation assay, the in vitro bacterial DNA repair assay, the in vitro forward gene mutation assay in mouse lymphoma cells, the in vitro chromosomal aberration assay in Chinese hamster lung (CHL) cells, the in vivo micronucleus assay in mice, and the unscheduled DNA synthesis assay in rats. Aripiprazole and a metabolite (2,3-DCPP) were clastogenic in the in vitro chromosomal aberration assay in CHL cells with and without metabolic activation. The metabolite, 2,3-DCPP, produced increases in numerical aberrations in the in vitro assay in CHL cells in the absence of metabolic activation. A positive response was obtained in the in vivo micronucleus assay in mice; however, the response was due to a mechanism not considered relevant to humans.

Impairment of Fertility

Female rats were treated with oral doses of 2, 6, and 20 mg/kg/day (0.6, 2, and 6 times the MRHD on a mg/m^2 basis) of aripiprazole from 2 weeks prior to mating through Day 7 of gestation. Estrus cycle irregularities and increased corpora lutea were seen at all doses, but no impairment of fertility was seen. Increased pre-implantation loss was seen at 6 and 20 mg/kg/day and decreased fetal weight was seen at 20 mg/kg/day.

Male rats were treated with oral doses of 20, 40, and 60 mg/kg/day (6, 13, and 19 times the MRHD on mg/m^2 basis) of aripiprazole from 9 weeks prior to mating through mating. Disturbances in spermatogenesis were seen at 60 mg/kg and prostate atrophy was seen at 40 and 60 mg/kg, but no impairment of fertility was seen.

13.2 Animal Toxicology and/or Pharmacology

Oral Aripiprazole

Aripiprazole produced retinal degeneration in albino rats in a 26-week chronic toxicity study at a dose of 60 mg/kg and in a 2-year carcinogenicity study at doses of 40 and 60 mg/kg. The 40 and 60 mg/kg/day doses are 13 and 19 times the MRHD based on mg/m^2 and 7 to 14 times human exposure at MRHD based on AUC. Evaluation of the retinas of albino mice and of monkeys did not reveal evidence of retinal degeneration. Additional studies to further evaluate the mechanism have not been performed. The relevance of this finding to human risk is unknown.

Intramuscular Aripiprazole

The toxicological profile for aripiprazole administered to experimental animals by intramuscular injection is generally similar to that seen following oral administration at comparable plasma levels of the drug. With intramuscular injection, however, injection-site tissue reactions are observed that consist of localized inflammation, swelling, scabbing and foreign-body reactions to deposited drug. These effects gradually resolved with discontinuation of dosing.

After 26 weeks of treatment in rats, the no-observed-adverse-effect level (NOAEL) was 50 mg/kg in male rats and 100 mg/kg in female rats, which are approximately 1 and 2 times, respectively, the maximum recommended human 400-mg dose of aripiprazole extended-release injectable suspension on a mg/m^2 body surface area. At the NOAEL in rats, the AUC7d values were 14.4 mcg∙h/mL in males and 104.1 mcg∙h/mL in females. In dogs at 52 weeks of treatment at the NOAEL of 40 mg/kg, which is approximately 3 times the MRHD (400 mg) on a mg/m^2 body surface area, the AUC7d values were approximately 59 mcg∙h/mL in males and 44 mcg∙h/mL in females. In patients at the MRHD of 400 mg, the AUCτ (0-28 days) was 163 mcg∙h/mL. For comparison to this human AUC, extrapolating the animal AUC7d values to an AUC28d results in AUC28d values of approximately 58 and 416 mcg∙h/mL for male and female rats, respectively, and 236 and 175 mcg∙h/mL for male and female dogs, respectively.

14 CLINICAL STUDIES

14.1 Schizophrenia

The efficacy of ABILIFY MAINTENA for treatment of schizophrenia was established in:

- One short-term (12-week), randomized, double-blind, placebo-controlled trial in acutely relapsed adults, Protocol 31-12-291 (Study 1)
- One longer-term, double-blind, placebo-controlled, randomized-withdrawal (maintenance) trial in adults, Protocol 31-07-246 (Study 2).

Short-Term Efficacy

In the short-term (12-week), randomized, double-blind, placebo-controlled trial in acutely relapsed adults (Study 1), the primary measure used for assessing psychiatric signs and symptoms was the Positive and Negative Syndrome Scale (PANSS). The PANSS is a 30-item scale that measures positive symptoms of schizophrenia (7 items), negative symptoms of schizophrenia (7 items), and general psychopathology (16 items), each rated on a scale of 1 (absent) to 7 (extreme); total PANSS scores range from 30 to 210. The primary endpoint was the change from baseline in PANSS total score to week 10.

The inclusion criteria for this short-term trial included adult inpatients who met DSM-IV-TR criteria for schizophrenia. In addition, all patients entering the trial must have experienced an acute psychotic episode as defined by both PANSS Total Score ≥80 and a PANSS score of >4 on each of four specific psychotic symptoms (conceptual disorganization, hallucinatory behavior, suspiciousness/persecution, unusual thought content) at screening and baseline. The key secondary endpoint was the change from baseline in Clinical Global Impression-Severity (CGI-S) assessment scale to week 10. The CGI-S rates the severity of mental illness on a scale of 1 (normal) to 7 (among the most extremely ill) based on the total clinical experience of the rater in treating patients with schizophrenia. Patients had a mean PANSS total score of 103 (range 82 to 144) and a CGI-S score of 5.2 (markedly ill) at entry.

In this 12-week study (n=339) comparing ABILIFY MAINTENA (n=167) to placebo (n=172), patients were administered ABILIFY MAINTENA 400 mg or placebo on Days 0, 28, and 56. The dose could be adjusted down and up within the range of 400 to 300 mg on a one-time basis. ABILIFY MAINTENA was superior to placebo in improving the PANSS total score at the end of week 10 (see Table 10).

Table 10: Schizophrenia Short-term Study
Study Number | Treatment Group | Primary Efficacy Measure: PANSS Total Score
Study Number |  | Mean Baseline Score (SD) | LS Mean Change from Baseline (SE) | Placebo-subtracted Difference [Difference (drug minus placebo) in least-squares mean change from baseline.] (95% CI)
Study 1 | ABILIFY MAINTENA (400 to 300 mg) | 102.4 (11.4) | -26.8 (1.6) | -15.1 (-19.4, -10.8)
 | Placebo | 103.4 (11.1) | -11.7 (1.6) | --
SD: standard deviation; SE: standard error; LS Mean: least-squares mean; CI: unadjusted confidence interval.

The change in PANSS total score by week is shown in Figure 24. ABILIFY MAINTENA also showed improvement in symptoms represented by CGI-S score mean change from baseline to week 10. The results of exploratory subgroup analyses by gender, race, age, ethnicity, and BMI were similar to the results of the overall population.

Figure 24: Weekly PANSS Total Score-Change in the 12-Week, Placebo-Controlled Study with ABILIFY MAINTENA

n = the number of patients remaining in the respective study arm at each time point

Longer-Term Efficacy

The efficacy of ABILIFY MAINTENA in maintaining symptomatic control in schizophrenia was established in a double-blind, placebo-controlled, randomized-withdrawal trial in adult patients (Study 2) who met DSM-IV-TR criteria for schizophrenia and who were being treated with at least one antipsychotic medication. Patients had at least a 3-year history of illness and a history of relapse or symptom exacerbation when not receiving antipsychotic treatment.

In addition to the PANSS and CGI-S, clinical ratings during this trial included the:

- Clinical Global Impression-Improvement (CGI-I) scale, a scale of 1 (very much improved) to 7 (very much worse) based on the change from baseline in clinical condition and
- Clinical Global Impression-Severity of Suicide (CGI-SS) scale, which is comprised of 2 parts: Part 1 rates the severity of suicidal thoughts and behavior on a scale of 1 (not at all suicidal) to 5 (attempted suicide) based on the most severe level in the last 7 days from all information available to the rater and Part 2 rates the change from baseline in suicidal thoughts and behavior on a scale of 1 (very much improved) to 7 (very much worse).

This trial included:

- A 4 to 6 week open-label, oral conversion phase for patients on antipsychotic medications other than aripiprazole. A total of 633 patients entered this phase.
- An open-label, oral aripiprazole stabilization phase (target dose of 10 mg to 30 mg once daily). A total of 710 patients entered this phase. Patients were 18 to 60 years old (mean 40 years) and 60% were male. The mean PANSS total score was 66 (range 33 to 124). The mean CGI-S score was 3.5 (mildly to moderately ill). Prior to the next phase, stabilization was required. Stabilization was defined as having all of the following for four consecutive weeks: an outpatient status, PANSS total score ≤80, CGI-S ≤4 (moderately ill), and CGI-SS score ≤2 (mildly suicidal) on Part 1 and ≤5 (minimally worsened) on Part 2; and a score of ≤4 on each of the following PANSS items: conceptual disorganization, suspiciousness, hallucinatory behavior, and unusual thought content.
- A minimum 12-week uncontrolled, single-blind ABILIFY MAINTENA stabilization phase (treatment with 400 mg of ABILIFY MAINTENA given every 4 weeks in conjunction with oral aripiprazole [10 mg to 20 mg/day] for the first 2 weeks). The dose of ABILIFY MAINTENA may have been decreased to 300 mg due to adverse reactions. A total of 576 patients entered this phase. The mean PANSS total score was 59 (range 30 to 80) and the mean CGI-S score was 3.2 (mildly ill). Prior to the next phase, stabilization was required (see above for the definition of stabilization) for 12 consecutive weeks.
- A double-blind, placebo-controlled randomized-withdrawal phase to observe for relapse (defined below). A total of 403 patients were randomized 2:1 to the same dose of ABILIFY MAINTENA they were receiving at the end of the stabilization phase, (400 mg or 300 mg administered once every 4 weeks) or placebo. Patients had a mean PANSS total score of 55 (range 31 to 80) and a CGI-S score of 2.9 (mildly ill) at entry. The dose could be adjusted up and down or down and up within the range of 300 to 400 mg on a one-time basis.

The primary efficacy endpoint was time from randomization to relapse. Relapse was defined as the first occurrence of one or more of the following criteria:

- CGI-I of ≥5 (minimally worse) and
  1. an increase on any of the following individual PANSS items (conceptual disorganization, hallucinatory behavior, suspiciousness, unusual thought content) to a score >4 with an absolute increase of ≥2 on that specific item since randomization or
  2. an increase on any of the following individual PANSS items (conceptual disorganization, hallucinatory behavior, suspiciousness, unusual thought content) to a score >4 and an absolute increase ≥4 on the combined four PANSS items (conceptual disorganization, hallucinatory behavior, suspiciousness, unusual thought content) since randomization
- Hospitalization due to worsening of psychotic symptoms (including partial hospitalization), but excluding hospitalization for psychosocial reasons
- CGI-SS of 4 (severely suicidal) or 5 (attempted suicide) on Part 1 and/or 6 (much worse) or 7 (very much worse) on Part 2, or
- Violent behavior resulting in clinically significant self-injury, injury to another person, or property damage.

A pre-planned interim analysis demonstrated a statistically significantly longer time to relapse in patients randomized to the ABILIFY MAINTENA group compared to placebo-treated patients and the trial was subsequently terminated early because maintenance of efficacy was demonstrated. The final analysis demonstrated a statistically significantly longer time to relapse in patients randomized to the ABILIFY MAINTENA group than compared to placebo-treated patients. The Kaplan-Meier curves of the cumulative proportion of patients with relapse during the double-blind treatment phase for ABILIFY MAINTENA and placebo groups are shown in Figure 25.

Figure 25: Kaplan-Meier Estimation of Cumulative Proportion of Patients with Relapse [This figure is based on a total of 80 relapse events.]

The key secondary efficacy endpoint, percentage of subjects meeting the relapse criteria, was statistically significantly lower in patients randomized to the ABILIFY MAINTENA group (10%) than in the placebo group (40%).

14.2 Bipolar I Disorder – Maintenance Monotherapy

The efficacy of ABILIFY MAINTENA for the maintenance treatment of bipolar I disorder was established in a 52-week, double-blind, placebo-controlled, randomized withdrawal trial in adult patients who were experiencing a manic episode at trial entry, met DSM-IV-TR criteria for bipolar I disorder, and had a history of at least one previous manic or mixed episode with manic symptoms of sufficient severity to require one of the following interventions: hospitalization and/or treatment with a mood stabilizer, and/or treatment with an antipsychotic agent.

Clinical ratings during this trial included:

- Young Mania Rating Scale (YMRS)-an 11-item, clinician-rated scale used to assess the degree of manic symptomatology, in a range with 0 representing no symptoms, and 60 representing worst symptoms.
- Montgomery-Asberg Depression Rating Scale (MADRS) – a 10-item clinician-related scale used to assess the degree of depressive symptomatology, with 1 representing no symptoms, and 60 representing worst symptoms.
- Clinical Global Impression Bipolar Version Severity of Illness (CGI-BP-S) a scale of 1 (normal, not at all ill) to 7 (very severely ill patient) based on the patient's severity of illness mania, depression, and overall bipolar illness.

This trial included:

- A 4 to 6 week, open-label, oral conversion phase for patients on treatments for bipolar I disorder other than aripiprazole. A total of 466 patients entered this phase.
- A 2 to 8 week, open-label, oral aripiprazole stabilization phase (target dose of 15 mg to 30 mg once daily). A total of 632 patients entered this phase. Patients were 18 to 65 years old (mean 40.7 years) and 60% were female. The mean (range) baseline scores were: YMRS total, 16.9 MADRS total, 5.7, and CGI-BP-S overall, 3.4 (mildly to moderately ill). Prior to the next phase, stabilization was required. Stabilization was defined as having all of the following at one bi-weekly visit: Outpatient status, YMRS total score ≤12, MADRS total score ≤12, no active suicidality; with active suicidality defined as a score of 4 or more on the MADRS item 10 OR an answer of "yes" on question 4 or 5 on the Columbia Suicide Severity Rating Scale (C-SSRS).
- A minimum 12-week, uncontrolled, single-blind ABILIFY MAINTENA stabilization phase (treatment with 400 mg of ABILIFY MAINTENA given every 4 weeks in conjunction with oral aripiprazole [10 mg to 20 mg/day] for the first 2 weeks). The dose of ABILIFY MAINTENA was allowed to be decreased to 300 mg due to adverse reactions. A total of 425 patients entered this phase. The mean (range) baseline scores were: YMRS total, 5.8, MADRS total 3.7, and CGI-BP-S overall, 2.1 (minimally ill). Prior to the next phase, stabilization was required (see above for the definition of stabilization) for 8 consecutive weeks starting at week 6.
- A double-blind, placebo-controlled, randomized-withdrawal phase to observe for recurrence to a mood episode (defined below) for up to 52 weeks. A total of 266 patients were randomized 1:1 to the same dose of ABILIFY MAINTENA they were receiving at the end of the stabilization phase, (400 mg or 300 mg administered once every 4 weeks) or placebo. The mean (range) baseline scores were: YMRS total, 2.8 (0 to 12), MADRS total, 2.7 (0 to 12), and CGI-S overall, 1.7 (minimally ill). The dose could be decreased to 300 mg for tolerability and returned once to 400 mg.

The primary efficacy endpoint was time from randomization to recurrence of any mood episode. Recurrence was defined as the first occurrence of one or more of the following criteria:

- Hospitalization for any mood episode OR
- Any of the following:
  - YMRS total score ≥15 OR
  - MADRS total score ≥15 OR
  - Clinical Global Impression - Bipolar Version-Severity (CGI-BP-S) score >4 (overall score) OR
- Serious adverse event (SAE) of worsening disease (bipolar I disorder) OR
- Discontinuation due to lack of efficacy or discontinuation due to an adverse event (AE) of worsening disease OR
- Clinical worsening with the need for addition of a mood stabilizer, antidepressant treatment, antipsychotic medication, and/or increase greater than the allowed benzodiazepine doses for treatment of symptoms of an underlying mood disorder OR
- Active suicidality, which is defined as a score of 4 or more on the MADRS item 10 OR an answer of "yes" on question 4 or 5 on the C-SSRS

Analysis demonstrated a statistically significantly longer time to recurrence of any mood episode in subjects randomized to the ABILIFY MAINTENA group than compared to placebo-treated subjects. The Kaplan-Meier curves of the time of recurrence to any mood episode during the double-blind treatment phase for ABILIFY MAINTENA and placebo groups are shown in Figure 26.

Figure 26: Kaplan-Meier Estimation of Cumulative Recurrence Rate for Any Mood Episode [This figure is based on a total of 103 recurrence events.]

Analysis by type of mood recurrence demonstrated a statistically significantly longer time to recurrence for both manic and mixed mood episodes in subjects treated with ABILIFY MAINTENA compared to those treated with placebo. There was no substantial difference between treatment groups in delaying time to recurrence of depressive mood episodes.

An examination of subgroups did not reveal any clear evidence of differential responsiveness on the basis of age, sex, or race.

16 HOW SUPPLIED/STORAGE AND HANDLING

How Supplied

Pre-filled Dual Chamber Syringe:

ABILIFY MAINTENA (aripiprazole) pre-filled dual chamber syringe for extended-release injectable suspension in single-dose syringes is available in 300 mg or 400 mg strength syringes. The pre-filled dual chamber syringe consists of a front chamber that contains the lyophilized powder of aripiprazole monohydrate and a rear chamber that contains sterile water for injection.

300 mg kit (NDC 59148-045-80) | - 300 mg, single-dose, pre-filled, dual chamber syringe containing ABILIFY MAINTENA (aripiprazole) for extended-release injectable suspension lyophilized powder and Sterile Water for Injection - One 23-gauge, 1-inch (25 mm) hypodermic safety needle with needle protection device for deltoid administration in non-obese patients - One 22-gauge, 1.5-inch (38 mm) hypodermic safety needle with needle protection device for gluteal administration in non-obese patients or deltoid administration in obese patients - One 21-gauge, 2-inch (51 mm) hypodermic safety needle with needle protection device for gluteal administration in obese patients
400 mg kit (NDC 59148-072-80) | - 400 mg, single-dose, pre-filled, dual chamber syringe containing ABILIFY MAINTENA (aripiprazole) for extended-release injectable suspension lyophilized powder and Sterile Water for Injection - One 23-gauge, 1-inch (25 mm) hypodermic safety needle with needle protection device for deltoid administration in non-obese patients - One 22-gauge, 1.5-inch (38 mm) hypodermic safety needle with needle protection device for gluteal administration in non-obese patients or deltoid administration in obese patients - One 21-gauge, 2-inch (51 mm) hypodermic safety needle with needle protection device for gluteal administration in obese patients

Single-Dose Vial:

ABILIFY MAINTENA (aripiprazole) extended-release injectable suspension in single-dose vials is available in 300 mg or 400 mg strength vials.

300 mg kit (NDC 59148-018-71) | - 300 mg, single-dose vial of ABILIFY MAINTENA (aripiprazole) extended-release injectable suspension lyophilized powder - 5 mL, single-dose vial of Sterile Water for Injection, USP - One 3 mL, luer lock syringe with pre-attached 21-gauge, 1.5-inch hypodermic safety needle with needle protection device - One 3 mL, luer lock disposable syringe with luer lock tip - One vial adapter - One 23-gauge, 1-inch (25 mm) hypodermic safety needle with needle protection device for deltoid administration in non-obese patients - One 22-gauge, 1.5-inch (38 mm) hypodermic safety needle with needle protection device for gluteal administration in non-obese patients or deltoid administration in obese patients - One 21-gauge, 2-inch (51 mm) hypodermic safety needle with needle protection device for gluteal administration in obese patients
300 mg kit (NDC 59148-232-12) | - 300 mg, single-dose vial of ABILIFY MAINTENA (aripiprazole) extended-release injectable suspension lyophilized powder - 2.5 mL, single-dose vial of Sterile Water for Injection, USP - One 3 mL, luer lock syringe with pre-attached 21-gauge, 1.5-inch hypodermic safety needle with needle protection device - One 3 mL, luer lock disposable syringe with luer lock tip - One vial adapter - One 23-gauge, 1-inch (25 mm) hypodermic safety needle with needle protection device for deltoid administration in non-obese patients - One 22-gauge, 1.5-inch (38 mm) hypodermic safety needle with needle protection device for gluteal administration in non-obese patients or deltoid administration in obese patients - One 21-gauge, 2-inch (51 mm) hypodermic safety needle with needle protection device for gluteal administration in obese patients
400 mg kit (NDC 59148-019-71) | - 400 mg, single-dose vial of ABILIFY MAINTENA (aripiprazole) extended-release injectable suspension lyophilized powder - 5 mL, single-dose vial of Sterile Water for Injection, USP - One 3 mL, luer lock syringe with pre-attached 21-gauge, 1.5-inch hypodermic safety needle with needle protection device - One 3 mL, luer lock disposable syringe with luer lock tip - One vial adapter - One 23-gauge, 1-inch (25 mm) hypodermic safety needle with needle protection device for deltoid administration in non-obese patients - One 22-gauge, 1.5-inch (38 mm) hypodermic safety needle with needle protection device for gluteal administration in non-obese patients or deltoid administration in obese patients - One 21-gauge, 2-inch (51 mm) hypodermic safety needle with needle protection device for gluteal administration in obese patients
400 mg kit (NDC 59148-245-12) | - 400 mg, single-dose vial of ABILIFY MAINTENA (aripiprazole) extended-release injectable suspension lyophilized powder - 2.5 mL, single-dose vial of Sterile Water for Injection, USP - One 3 mL, luer lock syringe with pre-attached 21-gauge, 1.5-inch hypodermic safety needle with needle protection device - One 3 mL, luer lock disposable syringe with luer lock tip - One vial adapter - One 23-gauge, 1-inch (25 mm) hypodermic safety needle with needle protection device for deltoid administration in non-obese patients - One 22-gauge, 1.5-inch (38 mm) hypodermic safety needle with needle protection device for gluteal administration in non-obese patients or deltoid administration in obese patients - One 21-gauge, 2-inch (51 mm) hypodermic safety needle with needle protection device for gluteal administration in obese patients

Storage

Pre-filled dual chamber syringe:

Store below 30°C [86°F]. Do not freeze. Protect the syringe from light by storing in the original package until time of use.

Vial:

Store at 25°C (77°F), excursions permitted between 15°C and 30°C (59°F to 86°F) [see USP Controlled Room Temperature].

17 PATIENT COUNSELING INFORMATION

Advise the patient to read the FDA-approved patient labeling (Medication Guide)

Neuroleptic Malignant Syndrome

Counsel patients about a potentially fatal adverse reaction, Neuroleptic Malignant Syndrome (NMS) that has been reported in association with administration of antipsychotic drugs. Advise patients, family members, or caregivers to contact a health care provider or report to the emergency room if they experience signs and symptoms of NMS [see Warnings and Precautions (5.3)].

Tardive Dyskinesia

Counsel patients on the signs and symptoms of tardive dyskinesia and to contact their health care provider if these abnormal movements occur [see Warnings and Precautions (5.4)].

Metabolic Changes

Educate patients about the risk of metabolic changes, how to recognize symptoms of hyperglycemia and diabetes mellitus, and the need for specific monitoring, including blood glucose, lipids, and weight [see Warnings and Precautions (5.5)].

Pathological Gambling and Other Compulsive Behaviors

Advise patients and their caregivers of the possibility that they may experience compulsive urges to shop, increased urges to gamble, compulsive sexual urges, binge eating and/or other compulsive urges and the inability to control these urges while taking aripiprazole. In some cases, but not all, the urges were reported to have stopped when the dose was reduced or stopped [see Warnings and Precautions (5.6)].

Orthostatic Hypotension and Syncope

Educate patients about the risk of orthostatic hypotension and syncope especially early in treatment, and also at times of re-initiating treatment or increases in dosage [see Warnings and Precautions (5.7)].

Leukopenia/Neutropenia

Advise patients with a pre-existing low WBC count or a history of drug-induced leucopenia/neutropenia that they should have their CBC monitored while receiving ABILIFY MAINTENA [see Warnings and Precautions (5.9)].

Potential for Cognitive and Motor Impairment

Inform patients that ABILIFY MAINTENA has the potential to impair judgment, thinking, or motor skills. Caution patients about performing activities requiring mental alertness, such as operating hazardous machinery, or operating a motor vehicle, until they are reasonably certain that ABILIFY MAINTENA therapy does not affect them adversely [see Warnings and Precautions (5.11)].

Heat Exposure and Dehydration

Educate patients regarding appropriate care in avoiding overheating and dehydration [see Warnings and Precautions (5.12)].

Concomitant Medication

Advise patients to inform their health care providers of any changes to their current prescription or over-the-counter medications since there is a potential for clinically significant interactions [see Drug Interactions (7)].

Pregnancy

Advise patients to notify their healthcare provider if they become pregnant or intend to become pregnant during treatment with ABILIFY MAINTENA. Advise patients that ABILIFY MAINTENA may cause extrapyramidal and/or withdrawal symptoms (agitation, hypertonia, hypotonia, tremor, somnolence, respiratory distress, and feeding disorder) in a neonate. Advise patients that there is a pregnancy exposure registry that monitors pregnancy outcomes in women exposed to ABILIFY MAINTENA during pregnancy [see Use in Specific Populations (8.1)].

Lactation

ABILIFY MAINTENA use during pregnancy may affect milk supply. Advise the lactating patient to discuss any plans for breastfeeding with their healthcare provider, and to monitor the breastfed infant for dehydration and lack of appropriate weight gain [see Use in Specific Populations (8.2)].

Distributed and marketed by Otsuka America Pharmaceutical, Inc., Rockville, MD 20850 USA

Marketed by Lundbeck, Deerfield, IL 60015 USA

ABILIFY MAINTENA is a trademark of Otsuka Pharmaceutical Co., Ltd.

©2025, Otsuka Pharmaceutical Co., Ltd., Tokyo, 101-8535 Japan

MEDICATION GUIDE
ABILIFY MAINTENA® (a-BIL-i-fy main-TEN-a)
(aripiprazole) for extended-release injectable suspension, for intramuscular use

What is the most important information I should know about ABILIFY MAINTENA?
ABILIFY MAINTENA may cause serious side effects, including:

- Increased risk of death in elderly people with dementia-related psychosis. ABILIFY MAINTENA increases the risk of death in elderly people who have lost touch with reality (psychosis) due to confusion and memory loss (dementia). ABILIFY MAINTENA is not for the treatment of people with dementia-related psychosis.

What is ABILIFY MAINTENA?
ABILIFY MAINTENA is a prescription medicine given by injection by a healthcare provider:

- for the treatment of schizophrenia in adults
- alone as maintenance treatment of bipolar I disorder in adults

It is not known if ABILIFY MAINTENA is safe and effective in children under 18 years of age.

Who should not receive ABILIFY MAINTENA?
Do not receive ABILIFY MAINTENA if you are allergic to aripiprazole or any of the ingredients in ABILIFY MAINTENA. See the end of this Medication Guide for a complete list of ingredients in ABILIFY MAINTENA.

Before receiving ABILIFY MAINTENA, tell your healthcare provider about all of your medical conditions, including if you:

- have never taken aripiprazole before
- have or had diabetes or high blood sugar or a family history of diabetes or high blood sugar
- have or had high levels of total cholesterol, LDL cholesterol, or triglycerides, or low levels of HDL cholesterol
- have or had low or high blood pressure
- have or had heart problems or a stroke
- have or had a low white blood cell count
- have or had seizures (convulsions)
- have problems that may affect you receiving an injection in your arm or buttocks
- are pregnant or plan to become pregnant. It is not known if ABILIFY MAINTENA will harm your unborn baby. Receiving ABILIFY MAINTENA during your third trimester of pregnancy may cause your baby to have abnormal muscle movements or withdrawal symptoms after birth. Talk to your healthcare provider about the risk to your unborn baby if you receive ABILIFY MAINTENA during pregnancy
  - Tell your healthcare provider right away if you become pregnant or think that you are pregnant during treatment with ABILIFY MAINTENA.
  - If you become pregnant while receiving ABILIFY MAINTENA, talk to your healthcare provider about registering with the National Pregnancy Registry for Atypical Antipsychotics. You can register by calling 1-866-961-2388 or go to http://womensmentalhealth.org/clinical-and-research-programs/pregnancyregistry/
- are breastfeeding or plan to breastfeed. ABILIFY MAINTENA can pass into your breast milk and it is not known if it may harm your baby. Talk to your healthcare provider about the best way to feed your baby if you receive ABILIFY MAINTENA.

Tell your healthcare provider about all the medicines you take, including prescription medicines and over-the-counter medicines, vitamins, and herbal supplements.
ABILIFY MAINTENA and other medicines may affect each other causing possible serious side effects. ABILIFY MAINTENA may affect the way other medicines work, and other medicines may affect how ABILIFY MAINTENA works.
Your healthcare provider can tell you if it is safe to receive ABILIFY MAINTENA with your other medicines. Do not start or stop any medicines during treatment with ABILIFY MAINTENA without talking to your healthcare provider first. Know the medicines you take. Keep a list of them to show your healthcare provider and pharmacist when you get a new medicine.

How should I receive ABILIFY MAINTENA?

- Follow your ABILIFY MAINTENA treatment schedule exactly as your healthcare provider tells you to.
- Your healthcare provider will tell you how much ABILIFY MAINTENA you will receive and when you will receive it.
- ABILIFY MAINTENA is an injection given in your arm or buttock by your healthcare provider 1 time every month.
- There are 2 ways to start (initiate) treatment with ABILIFY MAINTENA if you currently take an antipsychotic medicine by mouth (oral):
  - 1-day initiation: You will receive 2 injections of ABILIFY MAINTENA on your first day of treatment. Each injection will be given in a different injection site. You will also take 1 dose of aripiprazole by mouth.
  OR
  - 14-day initiation: You will receive 1 injection of ABILIFY MAINTENA. You will continue to take your oral aripiprazole or your current antipsychotic medicine by mouth for 14 days in a row.
- You should not miss a dose of ABILIFY MAINTENA. If you miss a dose for some reason, call your healthcare provider right away to discuss what you should do next.

What should I avoid while receiving ABILIFY MAINTENA?

- Do not drive a car, operate machinery, or do other dangerous activities until you know how ABILIFY MAINTENA affects you. ABILIFY MAINTENA may affect your judgement, thinking, or motor skills.
- Do not drink alcohol during treatment with ABILIFY MAINTENA.
- Do not become too hot or dehydrated during treatment with ABILIFY MAINTENA.
  - Do not exercise too much.
  - In hot weather, stay inside in a cool place if possible.
  - Stay out of the sun.
  - Do not wear too much clothing or heavy clothing.
  - Drink plenty of water.

What are the possible side effects of ABILIFY MAINTENA?
ABILIFY MAINTENA may cause serious side effects, including:

- See "What is the most important information I should know about ABILIFY MAINTENA?"
- Stroke (cerebrovascular problems) in elderly people with dementia-related psychosis that can lead to death.
- Neuroleptic malignant syndrome (NMS), a serious condition that can lead to death. Call your healthcare provider or go to the nearest emergency room right away if you have some or all of the following symptoms of NMS:

- high fever
- confusion
- changes in pulse, heart rate, and blood pressure

- stiff muscles
- sweating

- Uncontrolled body movements (tardive dyskinesia). ABILIFY MAINTENA may cause movements that you cannot control in your face, tongue, or other body parts. Tardive dyskinesia may not go away, even if you stop receiving ABILIFY MAINTENA. Tardive dyskinesia may also start after you stop receiving ABILIFY MAINTENA.
- Problems with your metabolism such as:
  - high blood sugar (hyperglycemia) and diabetes: Increases in blood sugar can happen in some people who receive ABILIFY MAINTENA. Extremely high blood sugar can lead to coma or death. If you have diabetes or risk factors for diabetes, such as being overweight or a family history of diabetes, your healthcare provider should check your blood sugar before you start receiving ABILIFY MAINTENA and during your treatment.
    Call your healthcare provider if you have any of these symptoms of high blood sugar while receiving ABILIFY MAINTENA:

- feel very thirsty
- feel very hungry
- feel sick to your stomach

- need to urinate more than usual
- feel weak or tired
- feel confused, or your breath smells fruity

- Increased fat levels (cholesterol and triglycerides) in your blood.
- Weight gain. You and your healthcare provider should check your weight regularly during treatment with ABILIFY MAINTENA.

- Unusual and uncontrollable (compulsive) urges. Some people receiving ABILIFY MAINTENA have had unusual strong urges to gamble and gambling that cannot be controlled (compulsive gambling). Other compulsive urges including sexual urges, shopping, and eating or binge eating. If you or your family members notice that you are having unusual urges or behaviors, talk to your healthcare provider.
- Decreased blood pressure (orthostatic hypotension). You may feel lightheaded or faint when you rise too quickly from a sitting or lying position.
- Falls. ABILIFY MAINTENA may make you sleepy or dizzy, may cause a decrease in your blood pressure when changing position (orthostatic hypotension), and can slow your thinking and motor skills which may lead to falls that can cause fractures or other injuries.
- Low white blood cell count. Your healthcare provider may do blood tests during your first few months of treatment with ABILIFY MAINTENA.
- Seizures (convulsions)
- Sleepiness, drowsiness, feeling tired, difficulty thinking and doing normal activities. See "What should I avoid while receiving ABILIFY MAINTENA?"
- Problems controlling your body temperature so that you feel too warm. See "What should I avoid while receiving ABILIFY MAINTENA?"
- Difficulty swallowing that can cause food or liquid to get into your lungs

The most common side effects of ABILIFY MAINTENA include: weight gain, restlessness or feeling like you need to move (akathisia), injection site pain, or sleepiness (sedation).
These are not all the possible side effects of ABILIFY MAINTENA.
Call your doctor for medical advice about side effects. You may report side effects to FDA at 1-800-FDA-1088.

General information about the safe and effective use of ABILIFY MAINTENA.
If you would like more information, talk with your healthcare provider. You can ask your pharmacist or healthcare provider for information about ABILIFY MAINTENA that is written for healthcare professionals.

What are the ingredients in ABILIFY MAINTENA?
Active ingredient: aripiprazole monohydrate
Inactive ingredients: carboxymethylcellulose sodium, mannitol, sodium phosphate monobasic monohydrate and sodium hydroxide
ABILIFY MAINTENA is a trademark of Otsuka Pharmaceutical Co., Ltd.
©2025, Otsuka Pharmaceutical Co., Ltd., Tokyo, 101-8535 Japan
For more information, go to www.ABILIFYMAINTENA.com or call 1-800-441-6763.

This Medication Guide has been approved by the U.S. Food and Drug Administration.

Revised: 03/2025

PRINCIPAL DISPLAY PANEL - 300 mg Vial Label

NDC 59148-018-70
Rx only
300 mg per vial

Abilify Maintena™ (aripiprazole)
for extended release injectable suspension
Single use only. Sterile. Discard any unused portion.
For deltoid or gluteal intramuscular injection only.
Usual Dosage: See package insert.

Manufactured by: Otsuka Pharmaceutical Co., Ltd.
Distributed and Marketed by: Otsuka America Pharmaceutical, Inc.
Marketed by: Lundbeck

PRINCIPAL DISPLAY PANEL - 5 mL Vial Label

NDC 59148-100-01

5mL

Sterile Water
for Injection, USP
For single use only.

Discard unused portion.

Store at 25 °C (77 °F), excursions
permitted between 15 °C and 30 °C
(59 °F to 86 °F) [See USP].

09US12L-1008
Rx only

PRINCIPAL DISPLAY PANEL - 300 mg Kit Carton

NDC 59148-018-71
Rx only

Attention: Dispense an enclosed Medication Guide to each patient.

300 mg
per vial

Single use only. Discard Unused Portion.

For deltoid or gluteal
intramuscular injection only.

Abilify Maintena™
(aripiprazole) for extended release injectable suspension

Keep out of reach of children. Each injection must be administered by a healthcare professional only.

To reconstitute: Add 1.5 mL of Sterile Water for Injection, USP (supplied in kit) to make injectable suspension containing 200 mg/mL.

Excess water will be left in the vial; discard vial with the unused portion.

PRINCIPAL DISPLAY PANEL - 400 mg Vial Label

NDC 59148-019-70
Rx only
400 mg per vial

Abilify Maintena™ (aripiprazole)
for extended release injectable suspension
Single use only. Sterile. Discard any unused portion.
For deltoid or gluteal intramuscular injection only.
Usual Dosage: See package insert.

Manufactured by: Otsuka Pharmaceutical Co., Ltd.
Distributed and Marketed by: Otsuka America Pharmaceutical, Inc.
Marketed by: Lundbeck

PRINCIPAL DISPLAY PANEL - 400 mg Kit Carton

NDC 59148-019-71
Rx only

Attention: Dispense an enclosed Medication Guide to each patient.

400 mg
per vial

Single use only. Discard Unused Portion.

For deltoid or gluteal
intramuscular injection only.

Abilify Maintena™
(aripiprazole) for extended release injectable suspension

Keep out of reach of children. Each injection must be administered by a healthcare professional only.

To reconstitute: Add 1.9 mL of Sterile Water for Injection, USP (supplied in kit) to make injectable suspension containing 200 mg/mL.

Excess water will be left in the vial; discard vial with the unused portion.

PRINCIPAL DISPLAY PANEL - 300 mg Syringe Label

NDC 59148-045-80

300 mg

Abilify Maintena®
(aripiprazole)
for extended release
injectable suspension
Single use only.
Sterile. Discard any
unused portion.
For deltoid or gluteal
intramuscular
injection only.
Usual Dosage:
See package insert.

516628AA

PRINCIPAL DISPLAY PANEL - 300 mg Syringe Carton

For deltoid or
gluteal intramuscular
injection only

NDC 59148-045-80

Abilify Maintena®
(aripiprazole) for extended release injectable suspension

300 mg PER PRE-FILLED
DUAL CHAMBER SYRINGE

Single use only.
Keep out of reach
of children.

Each injection must be administered by a healthcare professional only.
Attention: Dispense an enclosed Medication Guide to each patient.

Rx Only

PRINCIPAL DISPLAY PANEL - 400 mg Syringe Label

NDC 59148-072-80

400 mg

Abilify Maintena®
(aripiprazole)
for extended release
injectable suspension
Single use only.
Sterile. Discard any
unused portion.
For deltoid or gluteal
intramuscular
injection only.
Usual Dosage:
See package insert.

516629AA

PRINCIPAL DISPLAY PANEL - 400 mg Syringe Carton

For deltoid or
gluteal intramuscular
injection only

NDC 59148-072-80

Abilify Maintena®
(aripiprazole) for extended release injectable suspension

400 mg PER PRE-FILLED
DUAL CHAMBER SYRINGE

Single use only.
Keep out of reach
of children.

Each injection must be administered by a healthcare professional only.
Attention: Dispense an enclosed Medication Guide to each patient.

Rx Only

PRINCIPAL DISPLAY PANEL - 400 mg Vial Kit Carton

NDC 59148-245-12

Rx only

Attention: Dispense an enclosed Medication Guide to each patient.

400 mg
per vial

Single use only. Discard Unused Portion.

For deltoid or gluteal
intramuscular injection only.

Abilify Maintena®
(aripiprazole) for extended release injectable suspension

Keep out of reach of children. Each injection must be administered by a healthcare professional only.

To reconstitute: Add 1.9 mL of Sterile Water for Injection, USP (supplied in kit) to make injectable suspension containing 200 mg/mL.

Excess water will be left in the vial; discard vial with the unused portion.

PRINCIPAL DISPLAY PANEL - 300 mg Vial Kit Carton

NDC 59148-232-12

Rx only

Attention: Dispense an enclosed Medication Guide to each patient.

300 mg
per vial

Single use only. Discard Unused Portion.

For deltoid or gluteal
intramuscular injection only.

Abilify Maintena®
(aripiprazole) for extended release injectable suspension

Keep out of reach of children. Each injection must be administered by a healthcare professional only.

To reconstitute: Add 1.5 mL of Sterile Water for Injection, USP (supplied in kit) to make injectable suspension containing 200 mg/mL.

Excess water will be left in the vial; discard vial with the unused portion.